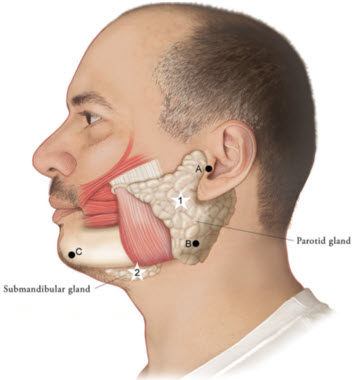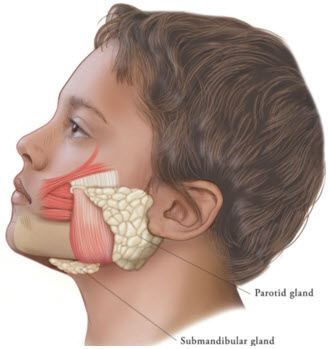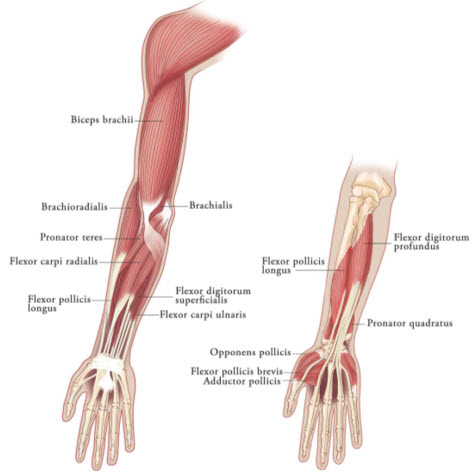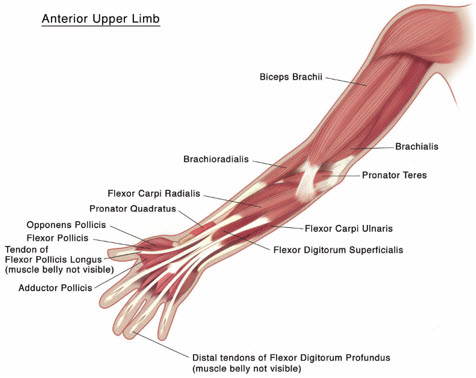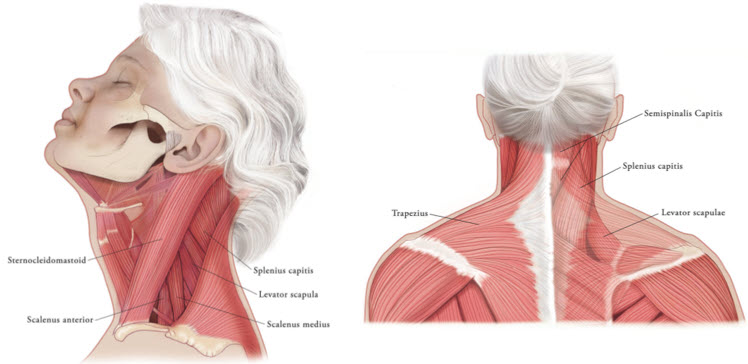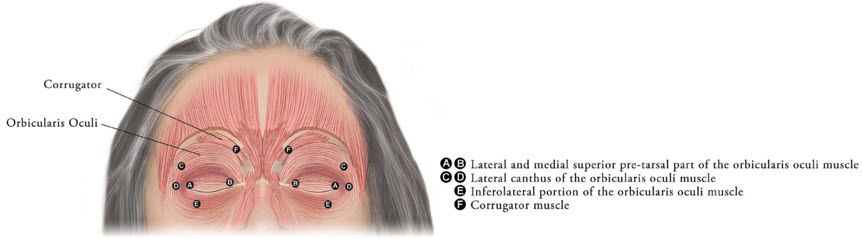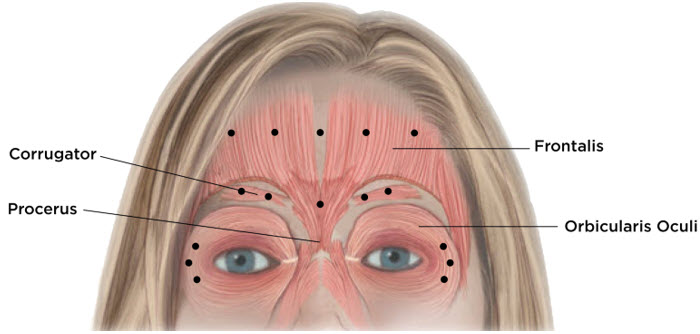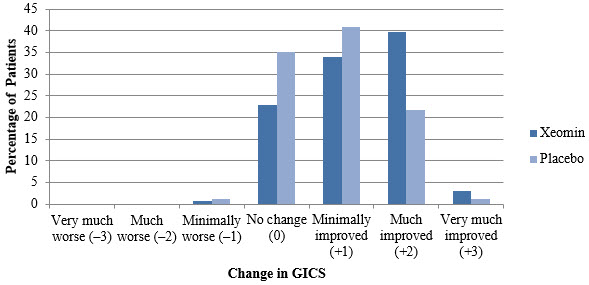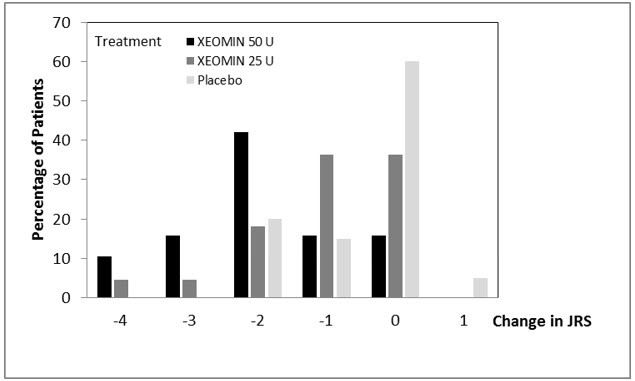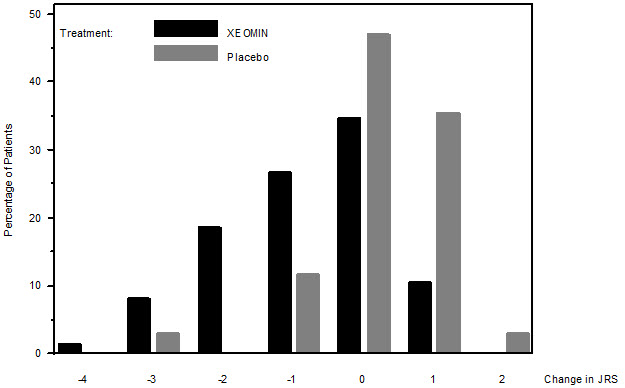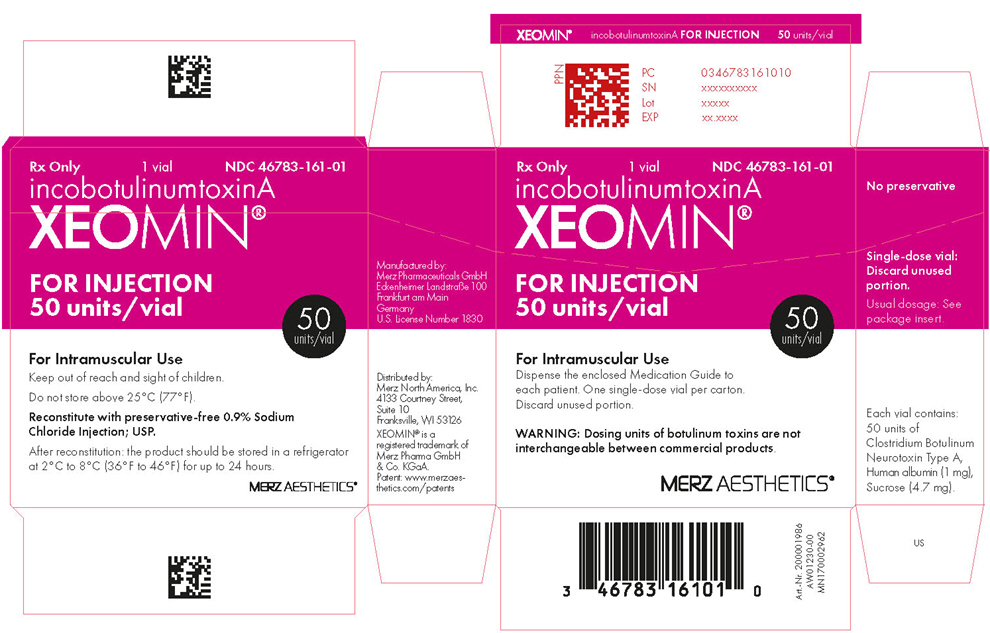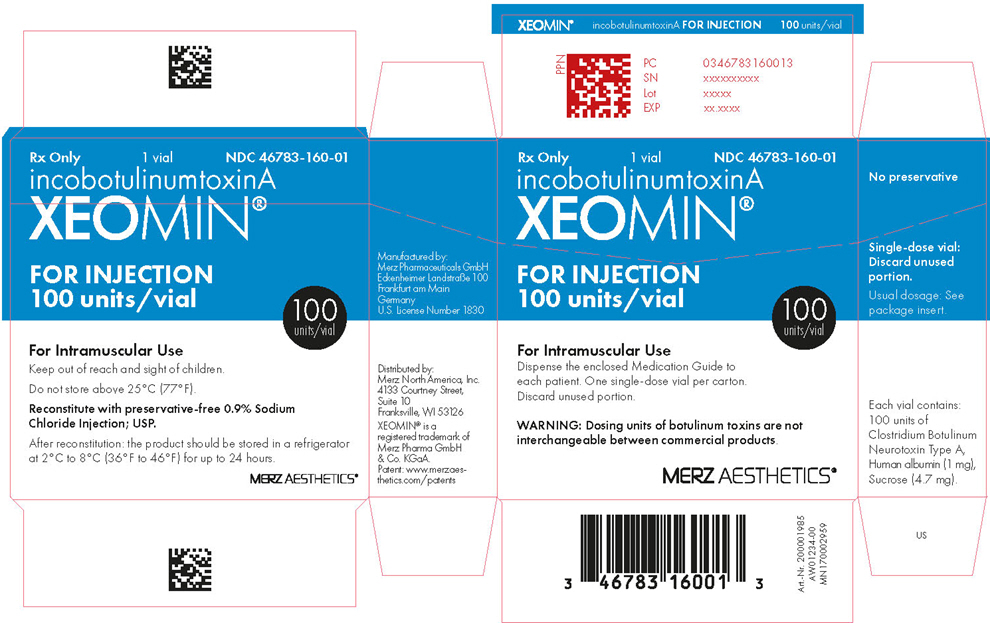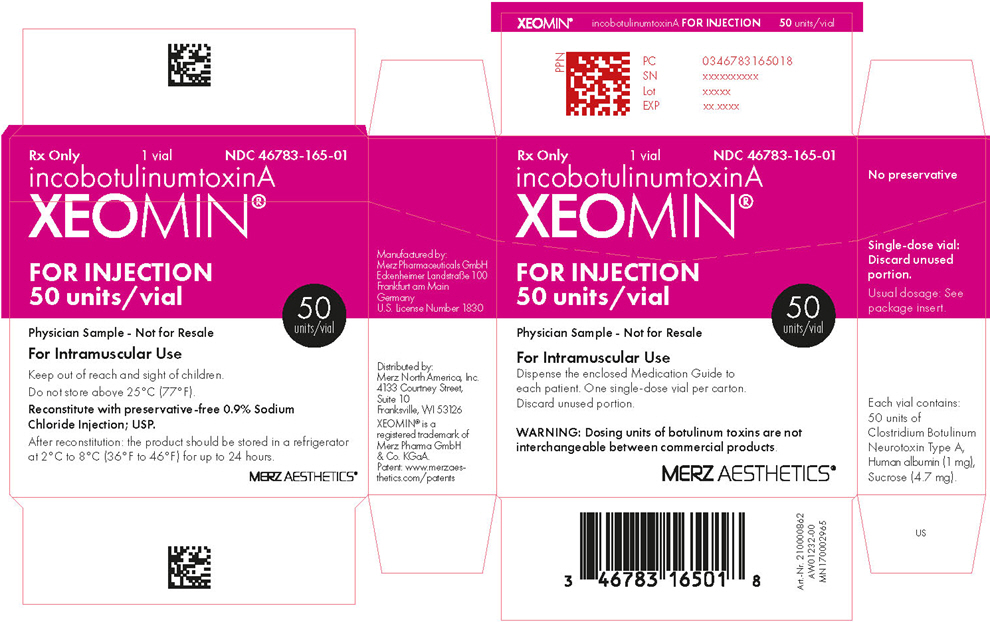 DRUG LABEL: Xeomin
NDC: 46783-161 | Form: INJECTION, POWDER, LYOPHILIZED, FOR SOLUTION
Manufacturer: Merz North America, Inc.
Category: prescription | Type: HUMAN PRESCRIPTION DRUG LABEL
Date: 20251219

ACTIVE INGREDIENTS: BOTULINUM TOXIN TYPE A 50 [USP'U]/1 1
INACTIVE INGREDIENTS: ALBUMIN HUMAN; SUCROSE

HIGHLIGHTS OF PRESCRIBING INFORMATION

These highlights do not include all the information needed to use XEOMIN® safely and effectively. See full prescribing information for XEOMIN.
XEOMIN (incobotulinumtoxinA) for injection, for intramuscular or intraglandular use
Initial U.S. Approval: 2010

WARNING: DISTANT SPREAD OF TOXIN EFFECT

See full prescribing information for complete boxed warning.

The effects of XEOMIN and all botulinum toxin products may spread from the area of injection to produce symptoms consistent with botulinum toxin effects. These symptoms have been reported hours to weeks after injection. Swallowing and breathing difficulties can be life threatening and there have been reports of death. The risk of symptoms is probably greatest in children treated for spasticity but symptoms can also occur in adults, particularly in those patients who have underlying conditions that would predispose them to these symptoms. (5.1)

RECENT MAJOR CHANGES

Indications and Usage (1.5) | 7/2024
Dosage and Administration (2.8) | 7/2024
Warnings and Precautions (5.8) | 9/2023

1 INDICATIONS AND USAGE

XEOMIN is an acetylcholine release inhibitor and neuromuscular blocking agent indicated for the treatment or improvement of:

- Chronic sialorrhea in patients 2 years of age and older (1.1)
- Upper limb spasticity in adults (1.2)
- Upper limb spasticity in pediatric patients 2 to 17 years of age, excluding spasticity caused by cerebral palsy (1.2)
- Cervical dystonia in adults (1.3)
- Blepharospasm in adults (1.4)
- the appearance of upper facial lines in adults:
  - moderate to severe glabellar lines associated with corrugator and/or procerus muscle activity (1.5)
  - moderate to severe horizontal forehead lines associated with frontalis muscle activity (1.5)
  - moderate to severe lateral canthal lines associated with orbicularis oculi muscle activity (1.5)

2 DOSAGE AND ADMINISTRATION

Chronic Sialorrhea:

- Chronic Sialorrhea in Adults: the recommended total dose is 100 Units per treatment session consisting of 30 Units per parotid gland and 20 Units per submandibular gland, no sooner than every 16 weeks (2.2)
- Chronic Sialorrhea in Pediatric Patients: the recommended dose is based on body weight administered in a 3:2 dose ratio into the parotid and submandibular glands, respectively, no sooner than every 16 weeks; ultrasound guidance recommended (2.2)

Upper limb spasticity, cervical dystonia, and blepharospasm: the optimum dose, frequency, and number of injection sites in the treated muscle(s) should be based on severity and prior treatment response in patients previously treated with botulinum toxin; individualize dosing for each patient:

- Upper Limb Spasticity in Adults: the recommended total dose is up to 400 Units, divided among affected muscles (2.3)
- Upper Limb Spasticity in Pediatric Patients, excluding spasticity caused by cerebral palsy: the recommended total dose is 8 Units/kg (maximum 200 Units) per single upper limb or 16 Units/kg (maximum 400 U) in both upper limbs, divided among affected muscles (2.3)
- Cervical Dystonia: the recommended initial dose is 120 Units per treatment session (2.4)
- Blepharospasm: the recommended initial dose is 50 Units (25 Units per eye) (2.5)

Upper Facial Lines (Glabellar Lines, Horizontal Forehead Lines, and Lateral Canthal Lines): When treating all three areas simultaneously (glabellar lines, horizontal forehead lines, and lateral canthal lines), the maximum recommended dose is 64 Units (2.6). When not treating simultaneously:

- Glabellar Lines: four Units into each of five sites, for a maximum dose of 20 Units
- Horizontal Forehead Lines treated simultaneously with Glabellar Lines: for HFL four Units into each of five sites (20 Units) and four Units into each of five GL sites (20 Units), for a maximum dose of 40 Units
- Lateral Canthal Lines: four Units into each of three sites per side (six injection sites in total), for a maximum dose of 12 Units per side (24 Units in total)

Administer retreatment with XEOMIN no more frequently than every three months.

Reconstituted XEOMIN:

- Is intended for intramuscular or intraglandular injection in the parotid and submandibular glands only (2.7)
- Use for only one injection session and for only one patient (2.7)
- Instructions are specific for 50 Unit, 100 Unit, and 200 Unit vials (2.7)
- Store in a refrigerator (2°C to 8°C) and use within 24 hours (2.7)

3 DOSAGE FORMS AND STRENGTHS

- For injection: 50 Units, 100 Units, or 200 Units lyophilized powder in a single-dose vial (3)

4 CONTRAINDICATIONS

- Known hypersensitivity to the active substance botulinum neurotoxin type A or to any of the excipients (4, 5.3)
- Infection at the proposed injection sites (4)

5 WARNINGS AND PRECAUTIONS

- Respiratory, speech, or swallowing difficulties: increased risk if bilateral neck muscle injections are needed, or with pre-existing muscular disorders; immediate medical attention may be required (5.1, 5.4)
- The potency Units of XEOMIN cannot be compared to or converted into Units of any other preparations of botulinum toxin products (5.2)
- Corneal exposure and ulceration: protective measures may be required (5.5)

6 ADVERSE REACTIONS

The most commonly observed adverse reactions at rates specified below and greater than placebo are:

Chronic Sialorrhea:

- Chronic Sialorrhea in Adults (≥4% of patients): tooth extraction, dry mouth, diarrhea, and hypertension (6.1)
- Chronic Sialorrhea in Pediatric Patients (≥1% of patients): bronchitis, headache, and nausea/vomiting (6.1)

Spasticity:

- Upper Limb Spasticity in Adults (≥2% of patients): seizure, nasopharyngitis, dry mouth, and upper respiratory tract infection (6.1)
- Upper Limb Spasticity in Pediatric Patients (≥3% of patients): nasopharyngitis and bronchitis (6.1)

Cervical Dystonia (≥5% of patients): dysphagia, neck pain, muscle weakness, injection site pain, and musculoskeletal pain (6.1)

Blepharospasm (≥10% of patients): eyelid ptosis, dry eye, visual impairment, and dry mouth (6.1)

Upper facial lines (Glabellar Lines, Horizontal Forehead Lines, and Lateral Canthal Lines): (>1% of patients): injection site bruising (6.1)

To report SUSPECTED ADVERSE REACTIONS, contact Merz Pharmaceuticals, LLC at 888-493-6646 or FDA at 1-800-FDA-1088 or www.fda.gov/medwatch.

7 DRUG INTERACTIONS

Aminoglycosides or other agents that interfere with neuromuscular transmission may potentiate the effect of XEOMIN; co-administer only with caution and close observation (7)

8 USE IN SPECIFIC POPULATIONS

- Pregnancy: based on animal data, may cause fetal harm (8.1)

FULL PRESCRIBING INFORMATION

WARNING: DISTANT SPREAD OF TOXIN EFFECT

Postmarketing reports indicate that the effects of XEOMIN and all botulinum toxin products may spread from the area of injection to produce symptoms consistent with botulinum toxin effects. These may include asthenia, generalized muscle weakness, diplopia, blurred vision, ptosis, dysphagia, dysphonia, dysarthria, urinary incontinence and breathing difficulties. These symptoms have been reported hours to weeks after injection. Swallowing and breathing difficulties can be life threatening and there have been reports of death. The risk of symptoms is probably greatest in children treated for spasticity but symptoms can also occur in adults treated for spasticity and other conditions, particularly in those patients who have underlying conditions that would predispose them to these symptoms. In unapproved uses, including lower limb spasticity in children, and in approved indications, cases of spread of effect have been reported at doses comparable to those used to treat cervical dystonia and at lower doses [see Warnings and Precautions (5.1)].

1 INDICATIONS AND USAGE

1.1 Chronic Sialorrhea

XEOMIN is indicated for the treatment of chronic sialorrhea in patients 2 years of age and older.

1.2 Upper Limb Spasticity

Upper Limb Spasticity in Adult Patients

XEOMIN is indicated for the treatment of upper limb spasticity in adult patients.

Upper Limb Spasticity in Pediatric Patients, Excluding Spasticity Caused by Cerebral Palsy

XEOMIN is indicated for the treatment of upper limb spasticity in pediatric patients 2 to 17 years of age, excluding spasticity caused by cerebral palsy.

1.3 Cervical Dystonia

XEOMIN is indicated for the treatment of cervical dystonia in adult patients.

1.4 Blepharospasm

XEOMIN is indicated for the treatment of blepharospasm in adult patients.

1.5 Upper Facial Lines (Glabellar Lines, Horizontal Forehead Lines, and Lateral Canthal Lines)

XEOMIN is indicated in adult patients for the temporary improvement in the appearance of upper facial lines:

- moderate to severe glabellar lines (GL) associated with corrugator and/or procerus muscle activity
- moderate to severe horizontal forehead lines (HFL) associated with frontalis muscle activity
- moderate to severe lateral canthal lines (LCL) associated with orbicularis oculi muscle activity.

2 DOSAGE AND ADMINISTRATION

2.1 Instructions for Safe Use

The potency Units of XEOMIN for injection are specific to the preparation and assay method utilized. Units of biological activity of XEOMIN cannot be compared to or converted into Units of any other botulinum toxin products assessed with any other specific assay method [see Warnings and Precautions (5.2) and Description (11)].

Reconstituted XEOMIN is intended for intramuscular or intra-salivary gland injection only.

Do not exceed the recommended maximum cumulative dose in a treatment session for any indication.

2.2 Recommended Dose for Chronic Sialorrhea

Chronic Sialorrhea in Adult Patients

The recommended total dose per treatment session is 100 Units. XEOMIN is injected into the parotid and submandibular glands on both sides (i.e., 4 injection sites per treatment session). The recommended total dose per treatment session is 100 Units. The dose is divided with a ratio of 3:2 between the parotid and submandibular glands (Table 1).

Figure 1: Glands for Injection in Chronic Sialorrhea in Adult Patients

Use the following guidelines if locating salivary glands using anatomic landmarks:

1) To inject the parotid gland, find the midpoint on the line connecting the tragus and mandible angle (Site A and B, respectively, Figure 1), approximately at the height of the ear lobe. Deliver the injection one finger breadth anterior to this site (Star 1, Figure 1).
2) To inject the submandibular gland, find the midpoint between the angle of the mandible and the tip of the chin (Site B and C, respectively, Figure 1). Deliver the injection one finger breadth medial to the inferior surface of the mandible at this site (Star 2, Figure 1).

Table 1: Dosing by Gland for Treatment of Chronic Sialorrhea in Adult Patients
Gland(s) | Units Per Side | Total
Parotid gland(s) | 30 Units | 60 Units
Submandibular gland(s) | 20 Units | 40 Units
Both Glands | 50 Units | 100 Units

The concentration used in the clinical study after reconstitution was 5 Units/0.1mL. Determine the timing for repeat treatment based on the actual clinical need of the individual patient, and no sooner than every 16 weeks.

Chronic Sialorrhea in Pediatric Patients

XEOMIN is injected into the parotid and submandibular glands on both sides (i.e., 4 injection sites per treatment session). Ultrasound imaging is recommended to guide needle placement into the salivary glands. The body-weight adjusted dose is divided with a ratio of 3:2 between the parotid and submandibular glands (Table 2). XEOMIN has not been studied in children weighing less than 12 kg [see Clinical Studies (14.1)].

Figure 2: Glands for Injection in Chronic Sialorrhea in Pediatric Patients

Table 2: Dosing by Body Weight Class for Treatment of Chronic Sialorrhea in Pediatric Patients
Body weight | Parotid gland, each side |  | Submandibular gland, each side |  | Total dose, both glands, both sides
Body weight | Dose per gland | Volume per injection | Dose per gland | Volume per injection | Total dose, both glands, both sides
12 kg or more to less than 15 kg | 6 Units | 0.24 mL | 4 Units | 0.16 mL | 20 Units
15 kg or more to less than 19 kg | 9 Units | 0.36 mL | 6 Units | 0.24 mL | 30 Units
19 kg or more to less than 23 kg | 12 Units | 0.48 mL | 8 Units | 0.32 mL | 40 Units
23 kg or more to less than 27 kg | 15 Units | 0.6 mL | 10 Units | 0.4 mL | 50 Units
27 kg or more to less than 30 kg | 18 Units | 0.72 mL | 12 Units | 0.48 mL | 60 Units
30 kg or more | 22.5 Units | 0.9 mL | 15 Units | 0.6 mL | 75 Units

The concentration used in the clinical study after reconstitution was 2.5 Units/0.1 mL. Determine the timing for repeat treatment based on the actual clinical need of the individual patient, and no sooner than every 16 weeks.

2.3 Recommended Dose for Upper Limb Spasticity

Upper Limb Spasticity in Adult Patients

Tailor the dosage, frequency, and number of injection sites to the individual patient based on the size, number, and location of muscles to be treated, severity of spasticity, presence of local muscle weakness, patient's response to previous treatment, and adverse event history with XEOMIN. Administer repeat XEOMIN treatments no sooner than every 12 weeks. In patients not previously treated with a botulinum toxin, begin initial dosing at the low end of the recommended dosing range and titrate as clinically necessary. Most patients in clinical studies were retreated between 12 and 14 weeks.

Table 3: XEOMIN Dosing by Muscle for Treatment of Adult Upper Limb Spasticity
Clinical Pattern Muscle | Units (Range) | Number of injection sites per muscle
Clenched Fist
Flexor digitorum superficialis | 25 Units-100 Units | 2
Flexor digitorum profundus | 25 Units-100 Units | 2
Flexed Wrist
Flexor carpi radialis | 25 Units-100 Units | 1-2
Flexor carpi ulnaris | 20 Units-100 Units | 1-2
Flexed Elbow
Brachioradialis | 25 Units-100 Units | 1-3
Biceps | 50 Units-200 Units | 1-4
Brachialis | 25 Units-100 Units | 1-2
Pronated Forearm
Pronator quadratus | 10 Units-50 Units | 1
Pronator teres | 25 Units-75 Units | 1-2
Thumb-in-Palm
Flexor pollicis longus | 10 Units-50 Units | 1
Adductor pollicis | 5 Units-30 Units | 1
Flexor pollicis brevis/Opponens pollicis | 5 Units-30 Units | 1

Figure 3: Muscles Involved In Adult Upper Limb Spasticity

Upper Limb Spasticity in Pediatric Patients, Excluding Spasticity Caused by Cerebral Palsy

Tailor the exact dosage, frequency, and number of injection sites to the individual patient based on size, number and localization of involved muscles; the severity of spasticity; and the presence of local muscle weakness.

The maximum recommended dose is 8 Units/kg, divided among affected muscles, up to a maximum dose of 200 Units per single upper limb. If both upper limbs are treated, do not exceed a total XEOMIN dosage of 16 Units/kg, up to a maximum of 400 Units.

Based on the selected dose, a reconstituted solution at a concentration between 1.25 Units/0.1 mL and 5 Units/0.1 mL is recommended [see Dosage and Administration (2.3)]. Determine the timing for repeat treatment based on the clinical need of the patient; administer repeat treatments no sooner than every 12 weeks. Most patients in clinical studies were retreated between 12 and 16 weeks.

Table 4 includes the recommended dose ranges for the treatment of the clinical patterns of flexed elbow, flexed wrist, pronated forearm, clenched fist, and thumb-in-palm.

Table 4: XEOMIN Dosing by Muscle for Treatment of Pediatric Upper Limb Spasticity, Excluding Spasticity Caused by Cerebral Palsy
Clinical Pattern Muscle | Dosage |  | Number of Injection Sites per Muscle
Clinical Pattern Muscle | Range (Units/kg) | Maximum (Units) | Number of Injection Sites per Muscle
Flexed Elbow
Brachioradialis | 1-2 | 50 | 1-2
Biceps | 2-3 | 75 | 1-3
Brachialis | 1-2 | 50 | 1-2
Flexed Wrist
Flexor carpi radialis | 1 | 25 | 1
Flexor carpi ulnaris | 1 | 25 | 1
Pronated Forearm
Pronator quadratus | 0.5 | 12.5 | 1
Pronator teres | 1-2 | 50 | 1-2
Clenched Fist
Flexor digitorum superficialis | 1 | 25 | 1
Flexor digitorum profundus | 1 | 25 | 1
Thumb-in-Palm
Flexor pollicis longus | 1 | 25 | 1
Adductor pollicis | 0.5 | 12.5 | 1
Flexor pollicis brevis/ opponens pollicis | 0.5 | 12.5 | 1

Figure 4: Muscles Injected for Pediatric Upper Limb Spasticity

2.4 Recommended Dose for Cervical Dystonia

The recommended initial dose of XEOMIN for cervical dystonia is 120 Units. In a placebo-controlled trial utilizing initial XEOMIN doses of 120 Units and 240 Units, no meaningful difference in effectiveness was demonstrated between the doses [see Clinical Studies (14.3)]. In previously treated patients, their past dose, response to treatment, duration of effect, and adverse event history should be taken into consideration when determining the XEOMIN dose.

In the treatment of cervical dystonia, XEOMIN is usually injected into the sternocleidomastoid, levator scapulae, splenius capitis, scalenus, and/or the trapezius muscle(s) (see Figure 5). This list is not exhaustive, as any of the muscles responsible for controlling head position may require treatment [see Clinical Studies (14.3)]. The dose and number of injection sites in each treated muscle should be individualized based on the number and location of the muscle(s) to be treated, the degree of spasticity/dystonia, muscle mass, body weight, and response to any previous botulinum toxin injections.

The frequency of XEOMIN repeat treatments should be determined by clinical response, but should generally be no more frequent than every 12 weeks [see Clinical Studies (14.3)].

Figure 5: Muscles Involved in Cervical Dsytonia

2.5 Recommended Dose for Blepharospasm

In treatment-naïve patients, the recommended initial dose of XEOMIN is 50 Units (25 Units per eye). In patients previously treated with a botulinum toxin A, consider their past dose, response to treatment, duration of effect, and adverse event history when determining the XEOMIN dose.

Do not exceed a total XEOMIN dose of 100 Units per treatment session (50 Units per eye).

Inject XEOMIN into the lateral and medial orbicularis oculi muscle of the upper lid; lateral canthus and the lateral orbicularis oculi muscle of the lower lid; and the corrugator muscle, if necessary (see Figure 6). The number and location of injections may be changed in response to adverse reactions or based on the patient's response to treatment, but do not exceed a total dose of 50 Units per eye.

Figure 6: Injection Sites for Blepharospasm

Determine the frequency of XEOMIN repeat treatments by clinical response but administer repeat treatments no more frequent than every 12 weeks [see Clinical Studies (14.4)].

2.6 Recommended Dose for Upper Facial Lines (Glabellar Lines, Horizontal Forehead Lines, and Lateral Canthal Lines)

The maximum recommended dose of XEOMIN for simultaneous treatment of upper facial lines [i.e., glabellar lines (GL), horizontal forehead lines (HFL) and lateral canthal lines (LCL)] in adult patients is 64 Units, comprised of 20 Units for GL, 20 Units for HFL, and 24 Units for LCL.

Administer retreatment with XEOMIN no more frequently than every three months.

When not treating upper facial lines (GL, HFL, and LCL) simultaneously in adult patients, refer to the following instructions:

Glabellar Lines

Equally distribute GL treatment to five equal intramuscular injections of 4 Units each. Inject 4 Units of reconstituted XEOMIN intramuscularly into each of 5 sites, 2 in each corrugator muscle and 1 in the procerus muscle for a maximum recommended dose of 20 Units (see Figure 7).

To reduce the complication of ptosis take the following steps:

- Avoid injection near the levator palpebrae superioris, particularly in patients with larger brow depressor complexes.
- Place corrugator injections at least 1 cm above the bony supraorbital ridge.

Horizontal Forehead Lines in Conjunction with Glabellar Lines

Treat HFL in conjunction with GL to minimize the potential for brow ptosis. The maximum recommended dose for treatment of HFL (20 Units) in conjunction with GL (20 Units) is 40 Units.

Equally distribute HFL treatment to 5 horizontally orientated intramuscular injection sites (4 Units each) into the frontalis muscle, at least 2 cm above the orbital rim (see Figure 7).

Lateral Canthal Lines

Inject 4 Units of reconstituted XEOMIN into 3 sites per side (6 total injection sites) in the lateral orbicularis oculi muscle for a total of 12 Units per side (24 Units overall). Place one injection in the horizontal extension of the lateral canthus approximately 1 cm lateral from the bony orbital rim. Place the other two injections approximately 1 cm above and below the area of the first injection (see Figure 7). Give injections with the needle bevel tip up and oriented away from the eye. Avoid injections too close to the zygomaticus major muscle to prevent lip ptosis.

Figure 7: Injection Sites for Upper Facial Lines (Glabellar Lines, Horizontal Forehead Lines, and Lateral Canthal Lines)

2.7 Preparation and Reconstitution Technique

Prior to injection, reconstitute each vial of XEOMIN with sterile, preservative-free 0.9% Sodium Chloride Injection, USP [see Dosage Form and Strengths (3)]. A 20-27 gauge short bevel needle is recommended for reconstitution. Draw up an appropriate amount of preservative-free 0.9% Sodium Chloride Injection, USP into a syringe (see Table 5). Clean the exposed portion of the rubber stopper of the vial with alcohol (70%) prior to insertion of the needle. After vertical insertion of the needle through the rubber stopper, the vacuum will draw the saline into the vial. Gently inject any remaining saline into the vial to avoid foam formation. If the vacuum does not pull the saline into the vial, then XEOMIN must be discarded. Remove the syringe from the vial and mix XEOMIN with the saline by carefully swirling and inverting/flipping the vial – do not shake vigorously. Reconstituted XEOMIN is a clear, colorless solution free of particulate matter. Do not use XEOMIN if the reconstituted solution has a cloudy appearance or contains floccular or particulate matter.

After reconstitution, use XEOMIN for only one injection session and for only one patient. Administer reconstituted XEOMIN within 24 hours after dilution. During this time period, store unused reconstituted XEOMIN in the original container in a refrigerator 2°C -8°C (36°F -46°F) for up to 24 hours until time of use. XEOMIN vials are for single-dose only. Discard any unused portion.

Diluent volumes for reconstitution of XEOMIN are indicated in Table 5.

Table 5: Diluent Volumes for Reconstitution of XEOMIN
Volume of preservative-free 0.9% Sodium Chloride Injection, USP | 50 Unit Vial: Resulting dose in Units per 0.1 mL | 100 Unit Vial: Resulting dose in Units per 0.1 mL | 200 Unit Vial: Resulting dose in Units per 0.1 mL
0.25 mL | 20 Units | - | -
0.5 mL | 10 Units | 20 Units | 40 Units
1 mL | 5 Units | 10 Units | 20 Units
1.25 mL | 4 Units | 8 Units | 16 Units
2 mL | 2.5 Units | 5 Units | 10 Units
2.5 mL | 2 Units | 4 Units | 8 Units
4 mL | 1.25 Units | 2.5 Units | 5 Units
5 mL | 1 Unit | 2 Units | 4 Units
8 mL [When using 8 mL of diluent for a 100 Unit or 200 Unit vial of XEOMIN, complete the following steps: 1. Reconstitute a 100 Unit or 200 Unit vial of XEOMIN with 4 mL of preservative-free 0.9% Sodium Chloride Injection, USP, following instructions above. 2. Withdraw 4 mL of preservative-free 0.9% Sodium Chloride Injection, USP, into an appropriately sized syringe for 8 mL in total. 3. Using the same syringe, draw up the 4 mL of XEOMIN solution from the reconstituted vial and mix gently.] | - | 1.25 Units | 2.5 Units
16 mL [When using 16 mL of diluent for a 200 Unit vial of XEOMIN, complete the following steps: 1. Reconstitute a 200 Unit vial of XEOMIN with 4 mL of preservative-free 0.9% Sodium Chloride Injection, USP, following instructions above. 2. Withdraw 12 mL of preservative-free 0.9% Sodium Chloride Injection, USP, into an appropriately sized syringe for 16 mL in total. 3. Using the same syringe, draw up the 4 mL of XEOMIN solution from the reconstituted vial and mix gently.] | - | - | 1.25 Units

2.8 Administration

Reconstituted XEOMIN is intended for intramuscular or intra-salivary gland injection only.

If proposed injection sites are marked with a pen, DO NOT inject XEOMIN through the pen marks; otherwise a permanent tattooing effect may occur.

For intramuscular injections, the number of injection sites is dependent upon the size of the muscle to be treated and the volume of reconstituted XEOMIN injected.

Inject XEOMIN carefully when injected at sites close to sensitive structures, such as the carotid artery, lung apices, and esophagus. Before administering XEOMIN, the healthcare provider should be familiar with the patient's anatomy and any anatomic alterations, e.g., due to prior surgical procedures.

Chronic Sialorrhea

Chronic Sialorrhea in Adult Patients

Use a sterile needle (e.g., 27-30 gauge (0.30-0.40 mm diameter), 12.5 mm length) for intra-salivary gland administration for the treatment of chronic sialorrhea. Inject XEOMIN close to the center of the gland.

The salivary glands can be located using ultrasound imaging or surface anatomical landmarks [see Dosage and Administration (2.3)].

Chronic Sialorrhea in Pediatric Patients

Use a sterile needle (e.g., 27-30 gauge (0.30-0.40 mm diameter), 12.5 mm length) for intra-salivary gland administration for the treatment of chronic sialorrhea. Inject XEOMIN close to the center of the gland.

Ultrasound guidance is recommended for the localization of the involved salivary glands [see Clinical Studies (14.2)].

Upper Limb Spasticity

Upper Limb Spasticity in Adult Patients

Use a sterile needle (e.g., 26-gauge (0.45 mm diameter), 37 mm length for superficial muscles; or 22-gauge (0.70 mm diameter), 75 mm length for deeper musculature) in the intramuscular administration in the treatment of upper limb spasticity in adults.

Localization of the involved muscles with electromyographic guidance, nerve stimulation, or ultrasound techniques is recommended.

Upper Limb Spasticity in Pediatric Patients, Excluding Spasticity Caused by Cerebral Palsy

Use a sterile needle (e.g., 30-gauge (0.30 mm diameter), 25 mm length for superficial muscles; or 27-gauge (0.40 mm diameter), 37 mm length for deeper musculature) in the intramuscular administration in the treatment of upper limb spasticity in pediatric patients.

Localization of the involved muscles with techniques such as electromyographic guidance, nerve stimulation, or ultrasound is recommended.

Cervical Dystonia

Use a sterile needle (e.g., 26-gauge (0.45 mm diameter), 37 mm length for superficial muscles; or 22-gauge (0.70 mm diameter), 75 mm length for deeper musculature) in the intramuscular administration in the treatment of cervical dystonia.

Localization of the involved muscles with electromyographic guidance, ultrasound, or nerve stimulation techniques may be useful.

Blepharospasm

Use a sterile needle (e.g., 30-gauge (0.40 mm diameter), 12.5 mm length) in the intramuscular administration in the treatment of blepharospasm.

Upper Facial Lines (Glabellar Lines, Horizontal Forehead Lines, and Lateral Canthal Lines)

Use a sterile needle [e.g., 30-33 gauge (0.3-0.2 mm diameter)], 13 mm length) for the intramuscular administration in the treatment of upper facial lines.

2.9 Monitoring to Assess Effectiveness

The median onset of XEOMIN treatment effect occurs within two to seven days after injection. The typical duration of effect of each treatment is up to 12-16 weeks; however, the duration of effect may vary in individual patients.

3 DOSAGE FORMS AND STRENGTHS

For injection: 50 Units, 100 Units, or 200 Units lyophilized powder in a single-dose vial for reconstitution only with preservative-free 0.9% Sodium Chloride Injection, USP.

4 CONTRAINDICATIONS

XEOMIN is contraindicated in patients with:

- Known hypersensitivity to any botulinum toxin product or to any of the components in the formulation [see Warnings and Precautions (5.3) and Description (11)].
- Infection at the proposed injection site(s) because it could lead to severe local or disseminated infection.

5 WARNINGS AND PRECAUTIONS

5.1 Spread of Toxin Effect

Postmarketing safety data from XEOMIN and other approved botulinum toxins suggest that botulinum toxin effects may, in some cases, be observed beyond the site of local injection. The symptoms are consistent with the mechanism of action of botulinum toxin and may include asthenia, generalized muscle weakness, diplopia, blurred vision, ptosis, dysphagia, dysphonia, dysarthria, urinary incontinence, and breathing difficulties. These symptoms have been reported hours to weeks after injection. Swallowing and breathing difficulties can be life threatening and there have been reports of death related to the spread of toxin effects. The risk of symptoms is probably greatest in children treated for spasticity but symptoms can occur in adults treated for spasticity and other conditions, and particularly in those patients who have underlying conditions that would predispose them to these symptoms. In unapproved uses, including lower limb spasticity in children, and in approved indications, symptoms consistent with spread of toxin effect have been reported at doses comparable to or lower than doses used to treat cervical dystonia.

Patients or caregivers should be advised to seek immediate medical care if swallowing, speech, or respiratory disorders occur.

5.2 Lack of Unit Equivalency Between Botulinum Toxin Products

The potency Units of XEOMIN are specific to the preparation and assay method utilized. Units of biological activity of XEOMIN cannot be compared to or converted into Units of any other botulinum toxin products assessed with any other specific assay method [see Description (11)].

5.3 Hypersensitivity Reactions

Serious hypersensitivity reactions have been reported with botulinum toxin products. Hypersensitivity reactions include anaphylaxis, serum sickness, urticaria, soft tissue edema, and dyspnea. If serious and/or immediate hypersensitivity reactions occur, discontinue further injection of XEOMIN and institute appropriate medical therapy immediately. The use of XEOMIN in patients with a known hypersensitivity to any botulinum neurotoxin or to any of the excipients (human albumin, sucrose), could lead to a life-threatening allergic reaction [see Contraindications (4)].

5.4 Dysphagia and Breathing Difficulties

Treatment with XEOMIN and other botulinum toxin products can result in swallowing or breathing difficulties. Patients with pre-existing swallowing or breathing difficulties may be more susceptible to these complications. In most cases, this is a consequence of weakening of muscles in the area of injection that are involved in breathing or swallowing. When distant effects occur, additional respiratory muscles may be involved [see Warnings and Precautions (5.4)].

Deaths as a complication of severe dysphagia have been reported after treatment with botulinum toxin. Dysphagia may persist for several months, and require use of a feeding tube to maintain adequate nutrition and hydration. Aspiration may result from severe dysphagia, and is a particular risk when treating patients in whom swallowing or respiratory function is already compromised.

Treatment of cervical dystonia with botulinum toxins may weaken neck muscles that serve as accessory muscles of ventilation. This may result in critical loss of breathing capacity in patients with respiratory disorders who may have become dependent upon these accessory muscles. There have been post-marketing reports of serious breathing difficulties, including respiratory failure, in patients with cervical dystonia treated with botulinum toxin products.

Patients with smaller neck muscle mass and patients who require bilateral injections into the sternocleidomastoid muscles have been reported to be at greater risk of dysphagia. In general, limiting the dose injected into the sternocleidomastoid muscle may decrease the occurrence of dysphagia.

Patients treated with botulinum toxin may require immediate medical attention should they develop problems with swallowing, speech or respiratory disorders. These reactions can occur within hours to weeks after injection with botulinum toxin [see Warnings and Precautions (5.1) and Adverse Reactions (6.1)].

Patients with neuromuscular disorders with peripheral motor neuropathic diseases, amyotrophic lateral sclerosis, or neuromuscular junctional disorders (e.g., myasthenia gravis or Lambert-Eaton syndrome) may be at increased risk for severe dysphagia and respiratory compromise from typical doses of XEOMIN.

5.5 Corneal Exposure, Corneal Ulceration, and Ectropion in Patients Treated for Blepharospasm

Reduced blinking from injection of botulinum toxin products in the orbicularis muscle can lead to corneal exposure, persistent epithelial defect, and corneal ulceration, especially in patients with VII nerve disorders. As patients with previous eye surgery may have reduced corneal sensation, carefully assess corneal sensation before treatment. Vigorous treatment of any corneal epithelial defect should be employed. This may require protective drops, ointment, therapeutic soft contact lenses, or closure of the eye by patching or other means. Because of its anticholinergic effects, XEOMIN should be used with caution in patients at risk of developing narrow angle glaucoma. To decrease the risk for ectropion, XEOMIN should not be injected into the medial lower eyelid area.

Ecchymosis easily occurs in the soft tissues of the eyelid. Immediate gentle pressure at the injection site can limit the size.

5.6 Risk of Ptosis in Patients Treated for Glabellar Lines

Do not exceed the recommended dosage and frequency of administration of XEOMIN.

In order to reduce the complication of ptosis the following steps should be taken:

- Avoid injection near the levator palpebrae superioris, particularly in patients with larger brow depressor complexes.
- Corrugator injections should be placed at least 1 cm above the bony supraorbital ridge.

5.7 Human Albumin and Transmission of Viral Diseases

This product contains albumin, a derivative of human blood. Based on effective donor screening and product manufacturing processes, it carries an extremely remote risk for transmission of viral diseases and variant Creutzfeldt-Jakob disease (vCJD). There is a theoretical risk for transmission of Creutzfeldt-Jakob disease (CJD), but if that risk actually exists, the risk of transmission would also be considered extremely remote. No cases of transmission of viral diseases, CJD, or vCJD have ever been identified for licensed albumin or albumin contained in other licensed products.

5.8 Pre-existing Conditions at the Injection Site

Use caution when XEOMIN is used where the targeted muscle shows excessive weakness or atrophy.

Use caution when XEOMIN is used in patients who have marked facial asymmetry, with surgical alterations to the facial anatomy, pre-existing eyelid or eyebrow ptosis, when excessive weakness or atrophy is present in the target muscles, excessive dermatochalasis, deep dermal scarring, thick sebaceous skin (e.g., the inability to substantially lessen glabellar lines even by physically spreading them apart).

6 ADVERSE REACTIONS

The following adverse reactions to XEOMIN are discussed in greater detail in other sections of the labeling:

- Spread of Effects from Toxin [see Warnings and Precautions (5.1)]
- Lack of Unit Equivalency between Botulinum Toxin Products [see Warnings and Precautions (5.2)]
- Hypersensitivity Reactions [see Warnings and Precautions (5.3)]
- Dysphagia and Breathing Difficulties [see Warnings and Precautions (5.4)]
- Corneal Exposure, Corneal Ulceration, and Ectropion in Patients Treated with XEOMIN for Blepharospasm [see Warnings and Precautions (5.5)]
- Risk of Ptosis in Patients Treated for Glabellar Lines [see Warnings and Precautions (5.6)]
- Human Albumin and Transmission of Viral Diseases [see Warnings and Precautions (5.7)]

6.1 Clinical Trials Experience

Because clinical trials are conducted under widely varying conditions, adverse reaction rates observed in the clinical trials of a drug cannot be directly compared to rates in the clinical trials of another drug and may not reflect the rates observed in practice.

Chronic Sialorrhea

Chronic Sialorrhea in Adult Patients

Table 6 lists the adverse reactions that occurred in ≥3% of XEOMIN-treated patients in the double-blind, placebo-controlled phase of the study in adult patients with chronic sialorrhea [see Clinical Studies (14.1)]. The most common adverse reactions (≥4%) were tooth extraction, dry mouth, diarrhea, and hypertension. In the controlled portion of this study, 74 patients received 100 Units of XEOMIN, and 36 patients received placebo. XEOMIN-treated patients were 21-80 years old (mean 65 years), and were predominantly male (71%) and White (99.5%).

Table 6: Adverse Reactions (≥3%) and Greater for XEOMIN than Placebo: Double-Blind Phase of the Placebo-Controlled Adult Chronic Sialorrhea Study
Adverse Reaction | XEOMIN 100 Units (N = 74) % | Placebo (N = 36) %
Tooth extraction | 5 | 0
Dry mouth | 4 | 0
Diarrhea | 4 | 3
Hypertension | 4 | 3
Fall | 3 | 0
Bronchitis | 3 | 0
Dysphonia | 3 | 0
Back pain | 3 | 0
Dry eye | 3 | 0

Chronic Sialorrhea in Pediatric Patients

Table 7 lists the adverse reactions that occurred in ≥1% of XEOMIN-treated patients 6-17 years of age in the double-blind, placebo-controlled portion of the study in pediatric patients with chronic sialorrhea [see Clinical Studies (14.1)]. Of the patients 6-17 years of age, 148 patients received a dose of XEOMIN according to body weight, and 72 patients received placebo. Thirty-five patients 2-5 years of age received an open-label dose of XEOMIN according to body weight. XEOMIN-treated patients were 2-17 years of age (mean 10 years), predominately male (63%) and White (100%).

Table 7: Adverse Reactions (≥1%) and Greater for XEOMIN than Placebo: Double-Blind Phase of the Placebo-Controlled Pediatric Chronic Sialorrhea Study
Adverse Reaction | XEOMIN (6-17 years) (N = 148) % | Placebo (6-17 years) (N = 72) %
Bronchitis | 1 | 0
Headache | 1 | 0
Nausea/Vomiting | 1 | 0

The most frequently reported adverse reaction in patients ages 2-5 years after XEOMIN injections was nasopharyngitis (6%).

In the open-label extension period, 222 patients 2-17 years of age received up to three additional treatments with XEOMIN every 16±2 weeks. The safety profile of XEOMIN during the open-label extension period was similar to that observed in the double-blind phase of the placebo-controlled pediatric chronic sialorrhea study.

Upper Limb Spasticity

Upper Limb Spasticity in Adult Patients

Table 8 lists the adverse reactions that occurred in ≥2% of XEOMIN-treated patients in two placebo-controlled studies in adult patients with upper limb spasticity. Study 1 and Study 2 were both double-blind, placebo-controlled studies, with an open-label extension [see Clinical Studies (14.2)]. In the controlled portion of these studies, 283 patients received ≥120 Units to 400 Units, of which 217 patients received at least 400 Units of XEOMIN, and 182 patients received placebo. XEOMIN-treated patients were 20-79 years of age (mean 56 years), and were predominantly male (58%), and White (84%).

Table 8: Adverse Reactions (≥2%) and Greater for XEOMIN than Placebo: Double-Blind Phase of Placebo-Controlled Adult Upper Limb Spasticity Study 1 and Study 2
Adverse Reaction | XEOMIN 400 Units (N = 217) % | Placebo (N = 182) %
Seizure | 3 | 0
Nasopharyngitis | 2 | 0
Dry mouth | 2 | 1
Upper respiratory tract infection | 2 | 1

Upper Limb Spasticity in Pediatric Patients

Table 9 lists the adverse reactions that occurred in ≥2% of XEOMIN-treated patients in Study 1 in pediatric patients 2 years of age and older with upper limb spasticity. In the controlled portion of Study 1, 350 patients were randomized to one of three doses of XEOMIN: 87 received 2 Units/kg per affected upper limb, 87 received 6 Units/kg per affected upper limb, and 176 received 8 Units/kg per affected upper limb [see Clinical Studies (14.2)]. XEOMIN-treated patients were 2 to 17 years of age (mean 7 years), 63% were male, and 90% were White.

No relationship between increased dose and increased occurrence of adverse reactions was observed. The most common adverse reactions (≥3% of XEOMIN-treated patients) at the recommended dose of XEOMIN (8 Units/kg) were nasopharyngitis and bronchitis.

Table 9: Adverse Reactions (≥2%) in Patients Treated with XEOMIN 2 Units/kg or 8 Units/kg: Double-Blind Phase of Study 1 in Pediatric Upper Limb Spasticity
Adverse Reactions | XEOMIN 2 Units/kg N=87 % | XEOMIN 8 Units/kg N=176 %
Infections and infestations
Nasopharyngitis | 6 | 3
Bronchitis | 2 | 3
Pharyngotonsillitis [Includes pharyngotonsillitis, pharyngitis and tonsillitis] | 2 | 2
Upper respiratory tract infection | 2 | 2
Respiratory tract infection viral | 1 | 2
Injury, poisoning and procedural complications
Fall | 0 | 2
Musculoskeletal and connective tissue disorders
Pain in extremity | 0 | 2

Cervical Dystonia

The data described below reflect exposure to a single intramuscular dose of XEOMIN in a placebo-controlled, Phase 3 trial in patients with cervical dystonia [see Clinical Studies (14.3)]. In this study, 159 patients received XEOMIN (78 were randomized to receive a total dose of 120 Units, and 81 were randomized to receive a total dose of 240 Units). XEOMIN-treated patients were 18 to 79 years old (mean 53 years), and were predominantly female (66%) and Caucasian (91%). At study baseline, approximately 25% had mild, 50% had moderate, and 25% had severe cervical dystonia. Approximately 61% of XEOMIN-treated patients had previously received another botulinum toxin type A product. Table 10 lists adverse reactions that occurred in ≥5% of XEOMIN-treated patients (in any treatment group) and greater than placebo.

Table 10: Adverse Reactions (≥5%) and Greater for XEOMIN than Placebo: Double-Blind Phase of the Placebo-Controlled Cervical Dystonia Study
Adverse Reaction | XEOMIN 120 Units (N=77) % | XEOMIN 240 Units (N=82) % | Placebo (N=74) %
Musculoskeletal and connective tissue disorders | 23 | 32 | 11
Neck pain | 7 | 15 | 4
Muscular weakness | 7 | 11 | 1
Musculoskeletal pain | 7 | 4 | 1
Gastrointestinal disorders | 18 | 24 | 4
Dysphagia | 13 | 18 | 3
Nervous system disorders | 16 | 17 | 7
General disorders and administration site conditions | 16 | 11 | 11
Injection site pain | 9 | 4 | 7
Infections and infestations | 14 | 13 | 11
Respiratory, thoracic and mediastinal disorders | 13 | 10 | 3

Blepharospasm

Study 1 was a randomized, double-blind, placebo-controlled study that only included treatment-naïve patients [see Clinical Studies (14.4)]. In the controlled portion, 22 patients received XEOMIN 25 Units, 19 patients received 50 Units, and 20 patients received placebo. XEOMIN-treated patients were 23 to 78 years of age (mean 55 years). Fifty-nine percent of the patients were women, 77% were Asian, and 23% White. No patients withdrew prematurely because of an adverse event. Table 11 lists the adverse reactions that occurred in ≥6% of XEOMIN-treated patients and greater than placebo.

Table 11: Adverse Reactions (≥6%) and Greater for XEOMIN than Placebo: Double-Blind Phase of the Placebo-Controlled Blepharospasm Study 1
Adverse Reaction | XEOMIN 50 U (N=19) % | Placebo (N=20) %
Eye disorders | 21 | 10
Eyelid ptosis | 16 | 0

Study 2 was a double-blind, placebo-controlled, flexible dose study with an open-label extension (OLEX) period. The study only included patients previously treated with onabotulinumtoxinA (Botox) [see Clinical Studies (14.4)]. In the controlled portion, 74 patients received XEOMIN at a mean dose of approximately 33 Units per eye (minimum 10 Units, maximum 50 Units). XEOMIN-treated patients were 22 to 79 years of age (mean 62 years), predominantly female (65%) and Caucasian (60%). Table 12 lists the adverse reactions that occurred in ≥5% of XEOMIN-treated patients and greater than placebo.

Table 12: Adverse Reactions (≥5%) and Greater for XEOMIN than Placebo: Double-Blind Phase of the Placebo-Controlled Blepharospasm Study 2
Adverse Reaction | XEOMIN (N=74) % | Placebo (N=34) %
Eye disorders | 38 | 21
Eyelid ptosis | 19 | 9
Dry eye | 16 | 12
Visual impairment [including vision blurred] | 12 | 6
Gastrointestinal disorders | 30 | 15
Dry mouth | 16 | 3
Diarrhea | 8 | 0
Infections and infestations | 20 | 15
Nasopharyngitis | 5 | 3
Respiratory tract infection | 5 | 3
Nervous system disorders | 14 | 9
Headache | 7 | 3
General disorders and administration site conditions | 11 | 9
Respiratory, thoracic and mediastinal disorders | 11 | 3
Dyspnea | 5 | 3

Upper Facial Lines [Glabellar Lines (GL), Horizontal Forehead Lines (HFL), and Lateral Canthal Lines (LCL)]

In two placebo-controlled trials in 730 adult subjects with upper facial lines (GL, HFL, and LCL), 545 subjects received up to 64 Units of XEOMIN and 185 subjects received placebo. XEOMIN-treated subjects were 19 to 76 years old and were predominantly female (82%). Adverse reactions were reported for 62 of the 545 XEOMIN-treated subjects (11%) and for 14 of the 185 placebo-treated subjects (8%).

The most frequent adverse reactions ≥1% and greater for XEOMIN than placebo are presented in Table 13.

Table 13: Adverse Reactions (≥1%) and Greater for XEOMIN than Placebo: Double-Blind Phase of the Placebo-Controlled Upper Facial Lines (GL, HFL, and LCL) Trials
 | Upper Facial Lines (GL, HFL, and LCL)
Adverse Reaction | XEOMIN N=545 % | Placebo N=185 %
Injection site bruising | 2 | 1

In the placebo-controlled trials, brow ptosis (0.7%) and injection site discomfort (0.6%) were also reported more frequently for XEOMIN than placebo-treated subjects.

In the two repeated dose upper facial lines (GL, HFL, and LCL) trials with up to three treatments of XEOMIN, adverse reactions were reported for 123 of the 720 subjects (17%). Injection site hematoma was the most common adverse reaction, reported in 8% of subjects, followed by headache (3%), injection site bruising (3%) and brow ptosis (1%). The incidence of these adverse reactions tended to decrease with subsequent treatments.

In both trials, all randomized subjects were followed up for 120 days before they could enter the open-label extension (OLEX) period which comprised two additional treatment cycles, with durations of 120 days each plus up to 30 days for eligibility reassessments per cycle. During OLEX period, eligible subjects received simultaneous upper facial lines injections of XEOMIN at a total dose of 64 U in all three facial areas (20 U in GL, 20 U in HFL, and 24 U in LCL area).

Glabellar Lines

In three placebo-controlled trials in 803 adult subjects with glabellar lines, 535 subjects received a single dose of 20 Units of XEOMIN and 268 subjects received placebo. XEOMIN-treated subjects were 24 to 74 years old, and were predominantly female (88%).

The most frequent adverse reactions ≥1% and greater for XEOMIN than Placebo are presented in Table 14.

Table 14: Adverse Reactions (≥1%) and Greater for XEOMIN than Placebo: Double-Blind Phase of the Placebo-Controlled Glabellar Lines Trials
Adverse Reaction | XEOMIN N=535 % | Placebo N=263 %
Nervous system disorders
Headache | 5 | 2

In the placebo-controlled trials, facial paresis (0.7%), injection site hematoma (0.6%) and eyelid edema (0.4%) were also reported more frequently for XEOMIN than placebo-treated subjects.

In open-label, multiple-dose trials, adverse reactions were reported for 105 of the 800 subjects (13%). Headache was the most common adverse reaction, reported in 7% of subjects, followed by injection site hematoma (1%). Adverse reactions reported in less than 1% of subjects were: facial paresis (brow ptosis), muscle disorder (elevation of eyebrow), injection site pain, and eyelid edema.

6.2 Postmarketing Experience

The following adverse reactions have been reported during post-approval use of XEOMIN. Because these reactions are reported voluntarily from a population of uncertain size, it is not always possible to reliably estimate their frequency or establish a causal relationship to drug exposure: allergic dermatitis, dysarthria, dysphagia, eye swelling, eyelid edema, flu-like symptoms, herpes zoster, hypersensitivity, injection site pain, injection site reaction, localized allergic reactions (e.g., swelling, edema, erythema, pruritus or rash), muscle spasm, muscular weakness, myalgia, nausea, and persistent dry mouth (> 110 days).

7 DRUG INTERACTIONS

7.1 Aminoglycosides and Other Agents Interfering with Neuromuscular Transmission

Co-administration of XEOMIN and aminoglycosides or other agents interfering with neuromuscular transmission (e.g., tubocurarine-type muscle relaxants) should only be performed with caution as these agents may potentiate the effect of the toxin.

7.2 Anticholinergic Drugs

Use of anticholinergic drugs after administration of XEOMIN may potentiate systemic anticholinergic effects.

7.3 Other Botulinum Neurotoxin Products

The effect of administering different botulinum toxin products at the same time or within several months of each other is unknown. Excessive neuromuscular weakness may be exacerbated by administration of another botulinum toxin prior to the resolution of the effects of a previously administered botulinum toxin.

7.4 Muscle Relaxants

Excessive weakness may also be exaggerated by administration of a muscle relaxant before or after administration of XEOMIN.

8 USE IN SPECIFIC POPULATIONS

8.1 Pregnancy

Risk Summary

There are no adequate data on the developmental risk associated with the use of XEOMIN in pregnant women. XEOMIN should be used during pregnancy only if the potential benefit justifies the potential risk to the fetus. XEOMIN was embryotoxic in rats and increased abortions in rabbits when given at doses higher than the maximum recommended human dose (MRHD) for cervical dystonia (120 Units), on a body weight basis.

In the U.S. general population, the estimated background risk of major birth defects and miscarriages in clinically recognized pregnancies is 2-4% and 15-20%, respectively. The background risk of major birth defects and miscarriage for the indicated population is unknown.

Data

Animal Data

When XEOMIN was administered intramuscularly to pregnant rats during organogenesis (3 Units/kg, 10 Units/kg, or 30 Units/kg on gestational days [GDs] 6, 12, and 19; or 7 Units/kg on GDs 6 to 19; or 2 Units/kg, 6 Units/kg, or 18 Units/kg on GDs 6, 9, 12, 16, and 19), decreases in fetal body weight and skeletal ossification were observed at doses that were also maternally toxic. The no-effect level for embryotoxicity in rats was 6 Units/kg (3 times the MRHD for cervical dystonia on a body weight basis). Intramuscular administration to pregnant rabbits during organogenesis (1.25 Units/kg, 2.5 Units/kg, or 5.0 Units/kg on GDs 6, 18, and 28) resulted in an increased rate of abortion at the highest dose, which was also maternally toxic. In rabbits, the no-effect level for increased abortion was 2.5 Units/kg (similar to the MRHD for cervical dystonia on a body weight basis).

8.2 Lactation

Risk Summary

There are no data on the presence of XEOMIN in human milk, the effects on the breastfed infant, or the effects on milk production. The developmental and health benefits of breastfeeding should be considered along with the mother's clinical need for XEOMIN and any potential adverse effects on the breastfed infant from XEOMIN or from the underlying maternal conditions.

8.4 Pediatric Use

The safety and effectiveness of XEOMIN have not been established in pediatric patients for the treatment of lower limb spasticity, cervical dystonia, and blepharospasm, or the temporary improvement in the appearance of upper facial lines:

- moderate to severe glabellar lines associated with corrugator and/or procerus muscle activity
- moderate to severe horizontal forehead lines associated with frontalis muscle activity
- moderate to severe lateral canthal lines associated with orbicularis oculi muscle activity [see Warnings and Precautions (5.1)].

Chronic Sialorrhea in Pediatric Patients

The safety and effectiveness of XEOMIN have been established by evidence from an adequate and well-controlled study of XEOMIN in patients 6 to 17 years of age with chronic sialorrhea [See Clinical Studies (14.1)]. Use of XEOMIN in patients 2 to 5 years of age is supported by the findings of efficacy and safety in patients 6 years and older with chronic sialorrhea, and by safety data in patients 2 to 5 years of age. Safety and effectiveness in pediatric patients below the age of 2 years have not been established [see Warnings and Precautions (5.1)].

Upper Limb Spasticity in Pediatric Patients, Excluding Spasticity Caused by Cerebral Palsy

Safety and effectiveness have been established in pediatric patients 2 to 17 years of age [see Warnings and Precautions (5.1), Adverse Reactions (6.1), and Clinical Studies (14.2)]. The safety and effectiveness of XEOMIN have been established by evidence from adequate and well-controlled studies of XEOMIN in patients 2 to 17 years of age with upper limb spasticity. A pediatric assessment for XEOMIN demonstrates that XEOMIN is safe and effective in another pediatric population. However, XEOMIN is not approved for such patient population due to marketing exclusivity for another botulinum toxin. Safety and effectiveness in pediatric patients below the age of 2 years have not been established [see Warnings and Precautions (5.1)].

Juvenile Animal Toxicity Data

In a study in which juvenile rats received intramuscular injections of Xeomin (0, 5, 10, or 30 Units/kg) every other week from postnatal day 21 for 10 weeks, decreased limb use, decreased body weight gain, skeletal muscle atrophy, and decreased bone growth and density were observed at all doses. Male reproductive organ histopathology (atrophy of the germinal epithelium of the testis, associated with hypospermia) was observed at the mid and high doses, and mating behavior was impaired at the high dose. A no-effect dose for adverse effects on development in juvenile animals was not established. The lowest dose tested (5 Units/kg) is less than the human dose of 400 Units on a body weight (kg) basis.

8.5 Geriatric Use

Chronic Sialorrhea

Of the total number of 184 patients in the placebo-controlled study in chronic sialorrhea in adult patients [see Clinical Studies (14.1)], 107 were 65 years of age and over (46 treated with XEOMIN 100 Units, 44 treated with XEOMIN 75 Units, and 17 received placebo). No differences in safety or effectiveness were observed between older and younger patients. Other clinical studies have not identified differences in responses between older and younger patients, but increased sensitivity in older patients cannot be ruled out.

Upper Limb Spasticity

Of the total number of 283 patients in the placebo-controlled studies in upper limb spasticity in adult patients [see Clinical Studies (14.2)], 118 were 65 years of age and over (70 treated with XEOMIN and 48 received placebo), which included 12 patients 75 years of age and over (7 treated with XEOMIN and 5 received placebo). No overall differences in safety or effectiveness were observed between older and younger adult patients. Other clinical studies have not identified differences in responses between older and younger adult patients, but increased sensitivity in older patients cannot be ruled out.

Cervical Dystonia

Of the total number of 233 patients in the placebo-controlled study in cervical dystonia [see Clinical Studies (14.3)], 29 were 65 years of age and over (19 treated with XEOMIN and 10 received placebo). Of these, ten XEOMIN-treated patients and four placebo-treated patients experienced an adverse event. For patients 65 years of age and over treated with XEOMIN, the most common adverse events were dysphagia (21%) and asthenia (11%).

Blepharospasm

Of the total number of 169 patients in the placebo-controlled studies in blepharospasm [see Clinical Studies (14.4)], 61 were 65 years of age and over (45 treated with XEOMIN and 16 received placebo). No overall difference in effectiveness was observed between older and younger patients.

Upper Facial Lines (Glabellar Lines, Horizontal Forehead Lines, and Lateral Canthal Lines)

Of the total number of 547 subjects in the placebo-controlled clinical studies for glabellar lines [see Clinical Studies (14.5)], 21 subjects were 65 years of age and over.

Of the total number of 730 subjects in the placebo-controlled clinical studies for upper facial lines GL, HFL, and LCL [see Clinical Studies (14.5)], 46 subjects were 65 years of age and over.

Clinical trials of XEOMIN showed no increase in the incidence of adverse events related to treatment with XEOMIN in patients 65 years of age and over but the trials did not include sufficient numbers of subjects 65 years of age and older to determine whether they respond differently from younger adult subjects.

10 OVERDOSAGE

Excessive doses of XEOMIN may be expected to produce neuromuscular weakness with a variety of symptoms, particularly when treated intramuscularly. Respiratory support may be required where excessive doses cause paralysis of the respiratory muscles. In the event of overdose, the patient should be medically monitored for symptoms of excessive muscle weakness or muscle paralysis [see Warnings and Precautions (5.1, 5.4)]. Symptomatic treatment may be necessary.

Symptoms of overdose are not likely to be present immediately following injection. Should accidental injection or oral ingestion occur, the person should be medically supervised for several weeks for signs and symptoms of excessive muscle weakness or paralysis.

There is no significant information regarding overdose from clinical studies of XEOMIN.

In the event of overdose, antitoxin raised against botulinum toxin is available from the Centers for Disease Control and Prevention (CDC) in Atlanta, GA. However, the antitoxin will not reverse any botulinum toxin-induced effects already apparent by the time of antitoxin administration. In the event of suspected or actual cases of botulinum toxin poisoning, please contact your local or state Health Department to process a request for antitoxin through the CDC. If you do not receive a response within 30 minutes, please contact the CDC directly at 770-488-7100. More information can be obtained at http://www.cdc.gov/ncidod/srp/drugs/formulary.html#1a.

11 DESCRIPTION

The active ingredient of XEOMIN is botulinum toxin type A produced from fermentation of Hall strain Clostridium botulinum serotype A. The botulinum toxin complex is purified from the culture supernatant and then the active ingredient is separated from the proteins (hemagglutinins and non-hemagglutinins) through a series of steps yielding the active neurotoxin with molecular weight of 150 kDa, without accessory proteins. XEOMIN is a sterile white to off-white lyophilized powder intended for intramuscular or intra-salivary gland injection after reconstitution with preservative-free 0.9% Sodium Chloride Injection, USP [see Dosage Forms and Strengths (3)]. One vial of XEOMIN contains 50 Units, 100 Units, or 200 Units of incobotulinumtoxinA, human albumin (1 mg), and sucrose (4.7 mg).

The primary release procedure for XEOMIN uses a cell-based potency assay to determine the potency relative to a reference standard. One Unit corresponds to the median intraperitoneal lethal dose (LD50) in mice. As the method for conducting the assay is specific to XEOMIN, Units of biological activity of XEOMIN cannot be converted into Units of any other botulinum toxin assessed with other specific assays.

12 CLINICAL PHARMACOLOGY

12.1 Mechanism of Action

XEOMIN blocks cholinergic transmission at the neuromuscular and salivary neuroglandular junction by inhibiting the release of acetylcholine from peripheral cholinergic nerve endings. This inhibition occurs according to the following sequence: neurotoxin binding to cholinergic nerve terminals, internalization of the neurotoxin into the nerve terminal, translocation of the light-chain part of the molecule into the cytosol of the nerve terminal, and enzymatic cleavage of SNAP25, a presynaptic target protein essential for the release of acetylcholine. In both muscles and glands, impulse transmission is re-established by the formation of new nerve endings.

12.3 Pharmacokinetics

Using currently available analytical technology, it is not possible to detect XEOMIN in the peripheral blood following intramuscular or intraglandular injection at the recommended doses.

12.6 Immunogenicity

As with all therapeutic proteins, there is a potential for immunogenicity.

The observed incidence of anti-drug antibodies is highly dependent on the sensitivity and specificity of the assay. Differences in assay methods preclude meaningful comparisons of the incidence of anti-drug antibodies in the studies described below with the incidence of anti-drug antibodies in other studies, including those of XEOMIN.

Of the 2649 patients treated with XEOMIN in clinical trials [see Clinical Studies (14)], 9 (0.3%) patients were positive for neutralizing antibodies after treatment whose antibody status at baseline was unknown and 4 (0.2%) additional patients developed neutralizing antibodies after treatment. No patients demonstrated a secondary lack of treatment response due to neutralizing antibodies.

Chronic Sialorrhea

Chronic Sialorrhea in Adult Patients

Of the 180 patients treated with XEOMIN in the main phase and extension period of the adult chronic sialorrhea clinical trial [see Clinical Studies (14.1)], 1 (0.6%) patient was positive for neutralizing antibodies after treatment. The patient had an antibody status unknown at baseline, and had not received a botulinum toxin treatment in the 12 months prior to enrollment in the study. No patients demonstrated a secondary lack of treatment response due to neutralizing antibodies.

Chronic Sialorrhea in Pediatric Patients

Of the 252 patients treated with XEOMIN in the main phase and open-label extension period of the pediatric chronic sialorrhea clinical trial [see Clinical Studies (14.1)], antibody measurements were only performed in patients with body weight of 30 kg or more, resulting in 80 patients tested for antibodies at baseline. Three patients tested positive for neutralizing antibodies at baseline and remained positive at the end of the study. No additional patients developed neutralizing antibodies, and none of the patients demonstrated a secondary lack of treatment response.

Upper Limb Spasticity

Upper Limb Spasticity in Adult Patients

Of the 456 patients treated with XEOMIN in the main phase and open-label extension period of the adult upper limb spasticity clinical trials (Study 1 and Study 2) [see Clinical Studies (14.2)], 4 patients were positive for neutralizing antibodies at baseline, and 2 (0.4%) additional patients (with unknown antibody status at baseline) were positive after treatment. Both patients had not received a botulinum toxin treatment in the 12 months prior to enrollment in the studies. No patients demonstrated a secondary lack of treatment response due to neutralizing antibodies.

Upper Limb Spasticity in Pediatric Patients

Of the 907 patients treated with XEOMIN in clinical trials for treatment of pediatric spasticity [see Clinical Studies (14.2)], 7 patients were positive for neutralizing antibodies at baseline, and 4 (0.4%) additional patients (with unknown antibody status at baseline) were positive after treatment. All of these patients were treated with onabotulinumtoxinA and/or abobotulinumtoxinA prior to enrollment in the study. Patients who had never received a botulinum toxin treatment did not develop neutralizing antibodies after being treated with XEOMIN. Antibody measurements were not performed in patients with <21 kg body weight. No patients demonstrated a secondary lack of treatment response due to neutralizing antibodies.

Cervical Dystonia

Of the 227 patients treated with XEOMIN in the main phase and open-label extension period of the cervical dystonia clinical trial [see Clinical Studies (14.3)], 5 patients were positive for neutralizing antibodies at baseline, 1 (0.4%) patient (with unknown antibody status at baseline) was positive after treatment, and 4 (1.8%) additional patients developed neutralizing antibodies after treatment. All of these patients were pre-treated with onabotulinumtoxinA and/or abobotulinumtoxinA prior to enrollment in the study. No patients demonstrated a secondary lack of treatment response due to neutralizing antibodies.

Blepharospasm

Of the 163 patients treated with XEOMIN in the main phase and open-label extension period of the blepharospasm clinical trials (Study 1 and Study 2) [see Clinical Studies (14.4)], 1 (0.6%) patient (with unknown antibody status at baseline) was positive for neutralizing antibodies after treatment. The patient had not received a botulinum toxin treatment in the 12 months prior to enrollment in the studies. No patients demonstrated a secondary lack of treatment response due to neutralizing antibodies.

Glabellar Lines

Of the 464 patients treated with XEOMIN in the main phase and open-label extension period of the glabellar lines clinical trials (GL-1 and GL-2) [see Clinical Studies (14.5)], no patients developed neutralizing antibodies after treatment. No patients demonstrated a secondary lack of treatment response due to neutralizing antibodies.

13 NONCLINICAL TOXICOLOGY

13.1 Carcinogenesis, Mutagenesis, Impairment of Fertility

Carcinogenesis

Studies to evaluate the carcinogenic potential of XEOMIN have not been conducted.

Mutagenesis

Genotoxicity studies have not been conducted for XEOMIN.

Impairment of Fertility

In a fertility and early embryonic development study in rabbits, males and females were dosed with XEOMIN (1.25 Units/kg, 2.5 Units/kg, or 3.5 Units/kg) intramuscularly every two weeks for 5 and 3 doses, respectively, beginning 2 weeks prior to mating. No effects on mating or fertility were observed. The highest dose tested is approximately twice the maximum recommended human dose for cervical dystonia (120 Units) on a body weight basis.

14 CLINICAL STUDIES

14.1 Chronic Sialorrhea

Chronic Sialorrhea in Adult Patients

The efficacy and safety of XEOMIN for the treatment of chronic sialorrhea in adult patients were evaluated in a double-blind, placebo-controlled clinical trial (NCT02091739) that enrolled a total of 184 patients with chronic sialorrhea resulting from Parkinson's disease, atypical parkinsonism, stroke, or traumatic brain injury, that was present for at least three months. Patients with a history of aspiration pneumonia, amyotrophic lateral sclerosis, salivary gland or duct malformation, and gastroesophageal reflux disease were excluded. The study consisted of a 16-week main phase, followed by an extension period of dose-blinded treatment with XEOMIN.

In the main phase, a fixed total dose of XEOMIN (100 Units or 75 Units) or placebo was administered into the parotid and submandibular salivary glands in a 3:2 dose ratio. The co-primary efficacy variables were the change in unstimulated Salivary Flow Rate (uSFR, Table 15) and the change in Global Impression of Change Scale (GICS, Table 16) at Week 4 post-injection. A total of 173 treated patients completed the main phase of the study. For both the uSFR and GICS, XEOMIN 100 Units was significantly better than placebo (see Table 15 and Table 16). XEOMIN 75 Units was not significantly better than placebo.

Table 15: Mean Change in uSFR (g/min) from Baseline at Week 4, 8, 12, and 16 of Main Phase
 | XEOMIN 100 Units | Placebo
 | N=73 | N=36
Week 4 [p=0.004] | -0.13 | -0.04
Week 8 | -0.13 | -0.02
Week 12 | -0.12 | -0.03
Week 16 | -0.11 | -0.01

Table 16: Mean GICS at Week 4, 8, 12, and 16 of Main Phase
 | XEOMIN 100 Units | Placebo
 | N=74 | N=36
Week 4 [p=0.002] | 1.25 | 0.67
Week 8 | 1.30 | 0.47
Week 12 | 1.21 | 0.56
Week 16 | 0.93 | 0.41

In the extension period, patients received up to three additional treatments with XEOMIN 100 Units or 75 Units every 16±2 weeks, for a total exposure duration of up to 64 weeks. Patients had periodic dental examinations to monitor for changes in dentition and oral mucosa. A total of 151 patients completed the extension period.

Chronic Sialorrhea in Pediatric Patients

The efficacy and safety of XEOMIN for the treatment of chronic sialorrhea in pediatric patients were evaluated in a prospective, randomized, double-blind, placebo-controlled (ages 6-17 years), parallel-group, multicenter trial (NCT02270736) that enrolled and treated a total of 216 pediatric patients 6-17 years of age with chronic sialorrhea associated with cerebral palsy, other genetic or congenital disorders, or traumatic brain injury. An additional 35 patients 2-5 years of age were treated with open-label XEOMIN in that study. The study consisted of a 16-week main phase, followed by an open-label extension period of treatment with XEOMIN where patients could receive up to 3 additional treatments with XEOMIN every 16 ± 2 weeks, for a total exposure duration of up to 64 weeks (222 patients completed the extension period).

In the main phase, patients 6-17 years of age were administered a total dose of XEOMIN according to body weight (up to 75 Units), or placebo, into the parotid and submandibular glands in a 3:2 dose ratio, using ultrasound guidance. Patients 2-5 years of age all received open-label treatment with XEOMIN, according to body weight, using ultrasound guidance. Patients with a body weight <12 kg were excluded.

The primary efficacy analysis was conducted in the 6-17 years of age patient group. The co-primary endpoints were the change in unstimulated Salivary Flow Rate (uSFR, Table 17) and carer's Global Impression of Change Scale (GICS, Table 18) at Week 4 post-injection.

For both the uSFR and GICS, XEOMIN was statistically significantly better than placebo (see Table 17 and Table 18).

Table 17: Mean change in uSFR (g/min) from Baseline at Week 4, 8, 12, and 16 of Main Phase
 | XEOMIN (6-17 years) N = 148 | Placebo (6-17 years) N=72
Week 4 [p=0.0012] | -0.14 | -0.07
Week 8 | -0.16 | -0.07
Week 12 | -0.16 | -0.06
Week 16 | -0.15 | -0.08

Table 18: Mean carer's GICS at Week 4, 8, 12, and 16 of Main Phase
 | XEOMIN (6-17 years) N = 148 | Placebo (6-17 years) N=72
Week 4 [p=0.0320] | 0.91 | 0.63
Week 8 | 0.94 | 0.54
Week 12 | 0.87 | 0.47
Week 16 | 0.77 | 0.38

Efficacy in pediatric patients 2 to 5 years of age is extrapolated from the finding of efficacy in older pediatric patients.

14.2 Upper Limb Spasticity

Upper Limb Spasticity in Adult Patients

The efficacy and safety of XEOMIN for the treatment of upper limb spasticity in adult patients were evaluated in two Phase 3, randomized, multi-center, double-blind studies.

Study 1 (NCT01392300) and Study 2 (NCT00432666) were both prospective, double-blind, placebo-controlled, randomized, multi-center trials with an open-label extension period (OLEX) to investigate the efficacy and safety of XEOMIN in the treatment of post-stroke spasticity of the upper limb. For patients who had previously received botulinum toxin treatment in any body region, Study 1 and Study 2 required that ≥12 months and ≥4 months, respectively, had passed since the most recent botulinum toxin administration.

Study 1 consisted of a 12-week main phase followed by three 12-week OLEX treatment cycles for a total exposure duration of 48 weeks. The study included 317 treatment-naïve patients who were at least three months post-stroke in the main study period (210 XEOMIN and 107 placebo). During the main period, XEOMIN (fixed total dose of 400 Units) and placebo were administered intramuscularly to the defined primary target clinical pattern chosen from among the flexed elbow, flexed wrist, or clenched fist patterns and to other affected muscle groups. 296 treated patients completed the main phase and participated in the first OLEX cycle. Each OLEX cycle consisted of a single treatment session (XEOMIN 400 Units total dose, distributed among all affected muscles) followed by a 12-week observation period.

Study 2 consisted of a 12-to-20-week main phase followed by an OLEX period of 48 – 69 weeks, for up to 89 weeks of exposure to XEOMIN. The study included 148 treatment-naïve and pre-treated patients with a confirmed diagnosis of post-stroke spasticity of the upper limb who were at least six months post-stroke (73 XEOMIN and 75 placebo). During the main period, for each patient, the clinical patterns of flexed wrist and clenched fist were treated with fixed doses (90 Units and 80 Units, respectively). Additionally, if other upper limb spasticity patterns were present, the elbow, forearm and thumb muscles could be treated with fixed doses of XEOMIN per muscle. 145 patients completed the main phase and participated in the OLEX period, during which time the dosing of each involved muscle could be adapted individually. During the main and OLEX periods, the maximum total dose per treatment session and 12-week interval was 400 Units.

The average XEOMIN doses injected into specific muscles and the number of injection sites per muscle in Study 1 and Study 2 are presented in Table 19.

Table 19: Doses Administered to Individual Muscles (Main Period) in Adult Upper Limb Spasticity Study 1 and Study 2 Intent to Treat (ITT)
Muscle Group | Muscle | Study 1 Units Injected | Injection Site Per Muscle | Study 2 Units Injected | Injection Site Per Muscle
 |  | XEOMIN (N=210) Mean±SD | XEOMIN Median (Min; Max) | XEOMIN (N=73) Mean±SD | XEOMIN Median (Min; Max)
All | Overall | 400 ± 2 Units | -- | 307 ± 77 Units | --
Elbow flexors | Overall | 151 ± 50 Units | 5 (1; 11) | 142 ± 30 Units | 5 (2; 9)
Elbow flexors | Biceps | 90 ± 21 Units | 3 (1; 4) | 80 ± 0 Units | 3 (2; 4)
Elbow flexors | Brachialis | 52 ± 26 Units | 2 (1; 4) | 50 ± 0 Units | 2 (1; 2)
Elbow flexors | Brachioradialis | 43 ± 16 Units | 2 (1; 3) | 60 ± 2Units | 2 (1; 3)
Wrist flexors | Overall | 112 ± 43 Units | 4 (1; 6) | 90 ± 0 Units | 4 (4; 4)
Wrist flexors | Flexor carpi radialis | 58 ± 22 Units | 2 (1; 3) | 50 ± 0 Units | 2 (2; 2)
Wrist flexors | Flexor carpi ulnaris | 56 ± 22 Units | 2 (1; 3) | 40 ± 0 Units | 2 (2; 2)
Finger flexors | Overall | 104 ± 35 Units | 4 (1; 4) | 80 ± 0 Units | 4 (4; 4)
Finger flexors | Flexor digitorum profundus | 54 ± 19 Units | 2 (1; 2) | 40 ± 0 Units | 2 (2; 2)
Finger flexors | Flexor digitorum superficialis | 54 ± 19 Units | 2 (1; 2) | 40 ± 0 Units | 2 (2; 2)
Forearm pronators | Overall | 52 ± 24 Units | 2 (1; 3) | 47 ± 16 Units | 2 (1; 3)
Forearm pronators | Pronator quadratus | 26 ± 13 Units | 1 (1; 1) | 25 ± 0 Units | 1 (1; 1)
Forearm pronators | Pronator teres | 42 ± 13 Units | 1 (1; 2) | 40 ± 0 Units | 1.5 (1; 2)
Thumb flexors/ adductors | Overall | 37 ± 25 Units | 2 (1; 4) | 25 ± 10 Units | 1.5 (1; 3)
Thumb flexors/ adductors | Adductor pollicis | 14 ± 8 Units | 1 (1; 1) | 10 ± 0 Units | 1 (1; 1)
Thumb flexors/ adductors | Flexor pollicis brevis / opponens pollicis | 14 ± 9 Units | 1 (1; 1) | 10 ± 0 Units | 1 (1; 1)
Thumb flexors/ adductors | Flexor pollicis longus | 26 ± 16 Units | 1 (1; 2) | 20 ± 0 Units | 1 (1; 1)

In Study 1, the primary efficacy variable was the change from baseline in Ashworth Scale (AS) score of the primary target clinical pattern determined by the investigator at the Week 4 visit. The Ashworth Scale is a clinical measure of the severity of spasticity by judging resistance to passive movement. The spasticity of the elbow flexors, wrist flexors, finger flexors, and thumb muscles as well as the forearm pronators was assessed on the 0 to 4-point Ashworth scale at each visit. The co-primary efficacy variable of Study 1 was the Investigator's Global Impression of Change Scales (GICS) after 4 Weeks of treatment with XEOMIN or placebo. The GICS is a global measure of a subject's functional improvement. Investigators were asked to evaluate the subject's global change in spasticity of the upper limb due to treatment, compared to the condition before the last injection. The response was assessed using a 7-point Likert scale that ranges from –3 (very much worse) to +3 (very much improved). XEOMIN was considered to be superior to placebo in Study 1 only if statistical significance was reached in both the AS and GICS variables.

The primary efficacy results are displayed in Table 20.

Table 20: Efficacy Results by Patterns of Spasticity in Adult Upper Limb Spasticity Study 1, Week 4
 | Mean Change in Ashworth Scale
 | XEOMIN (N=171) | Placebo (N=88)
Total Primary Target Clinical Pattern (flexed wrist, flexed elbow, and clenched fist) | -0.9 | -0.5
The analysis is based on Last Observation Carried Forward in the Intent To Treat population. p<0.001

A greater percentage of XEOMIN-treated subjects (43%) than placebo-treated subjects (23%) reported 'very much improved' and 'much improved' in their spasticity (see Figure 8).

Figure 8: Investigator's GICS in Adult Upper Limb Spasticity Study 1

Upper Limb Spasticity in Pediatric Patients

Study 1 (NCT02002884) was a prospective, double-blind, dose-response, randomized, multi-center trial with an open-label extension period to evaluate the efficacy and safety of XEOMIN for the treatment of upper limb spasticity in pediatric patients. Study 1 enrolled a total of 350 pediatric patients 2 to 17 years of age with upper limb spasticity in one or both upper limbs. In the double-blind main period of Study 1, patients were randomized to one of three dosages of XEOMIN: 2 Units/kg (maximum 50 Units per upper limb), 6 Units/kg (maximum 150 Units per upper limb); or 8 Units/kg (maximum 200 Units per upper limb). The maximum dose, if both upper limbs were treated, respectively was 4 Units/kg (maximum 100 Units), 12 Units/kg (maximum 300 Units), or 16 Units/kg (maximum 400 Units). For treatment of flexed elbow, injection of biceps brachii was mandatory. The investigator could select 1 of the 2 other muscles contributing to spasticity of elbow flexion (i.e., brachialis and brachioradialis) for injection. For patients needing treatment for a flexed wrist, both the flexor carpi radialis and flexor carpi ulnaris were injected. Study 1 used a dose-response design, in which the two highest dosages of XEOMIN (8 Units/kg and 6 Units/kg) were compared to the lowest dosage (2 Units/kg), which served as control. In the absence of a placebo control, the efficacy of the 2 Units/kg dosage of XEOMIN could not be evaluated in Study 1.

The co-primary efficacy variables in Study 1 were the change from baseline on the Ashworth Scale for the primary clinical target pattern (i.e., elbow flexors or wrist flexors), and the Investigator's Global Impression of Change Scale (GICS), both at Week 4. The GICS is a global measure of a subject's functional improvement based on a 7-point Likert scale that ranges from -3 = very much worse to +3 = very much improved.

As displayed in Table 21, the change from baseline in Ashworth Scale score was significantly greater for patients treated with XEOMIN 8 Units/kg than for patients treated with XEOMIN 2 Units/kg. The difference in GICS score between patients treated with XEOMIN 8 Units/kg and those treated with XEOMIN 2 Units/kg did not reach statistical significance. However, the clinical meaningfulness of the difference in Ashworth Scale score change between patients treated with XEOMIN 8 Units/kg and those treated with XEOMIN 2 Units/kg was established by a responder analysis, in which the proportion of patients with a 1-point change or greater on the Ashworth Scale was examined. In that analysis, 86% of patients treated with XEOMIN 8 Units/kg met the responder definition, compared to 71% of patients treated with XEOMIN 2 Units/kg (nominal p value = 0.0099).

There was no significant difference in change from baseline in Ashworth Scale score, GICS score, or proportion of responders between patients treated with XEOMIN 6 Units/kg and those treated with XEOMIN 2 Units/kg. Therefore, the efficacy of a 6 Units/kg dosage of XEOMIN for the treatment of upper limb spasticity in pediatric patients was not established in Study 1.

Table 21: Ashworth Scale and GICS Efficacy Results in Pediatric Upper Limb Spasticity Study 1, Week 4
 | XEOMIN 2 Units/kg (N=87) | XEOMIN 8 Units/kg (N=176)
Ashworth Scale
Mean Change from Baseline at Week 4 | -0.9 | -1.2
LS Mean Difference versus XEOMIN 2 Units/kg (95% CIs) | -- | -0.22 [p-value versus low dose group <0.05] (-0.40, -0.04)
GICS
Mean at Week 4 | 1.6 | 1.7
LS Mean Difference versus XEOMIN 2 Units/kg (95% CIs) | -- | 0.09 (-0.10, 0.28)
LS = Least Square Mean difference
CI = Confidence Interval

14.3 Cervical Dystonia

XEOMIN has been investigated in a randomized, double-blind, placebo-controlled, multicenter trial (NCT00407030) in a total of 233 patients with cervical dystonia. Patients had a clinical diagnosis of predominantly rotational cervical dystonia, with baseline Toronto Western Spasmodic Torticollis Rating Scale (TWSTRS) total score ≥20, TWSTRS severity score ≥10, TWSTRS disability score ≥3, and TWSTRS pain score ≥1. For patients who had previously received a botulinum toxin treatment for cervical dystonia, the trial required that ≥10 weeks had passed since the most recent botulinum toxin administration. Patients with swallowing disorders or any significant neuromuscular disease that might interfere with the study were excluded from enrollment. Patients were randomized (1:1:1) to receive a single administration of XEOMIN 240 Units (n=81), XEOMIN 120 Units (n=78), or placebo (n=74). Each patient received a single administration of 4.8 mL of reconstituted study agent (XEOMIN 240 Units, XEOMIN 120 Units, or placebo). The investigator at each site decided which muscles would receive injections of the study agent, the number of injection sites, and the volume at each site. The muscles most frequently injected were the splenius capitis/semispinalis, trapezius, sternocleidomastoid, scalene, and levator scapulae muscles. Table 22 indicates the average XEOMIN dose, and percentage of total dose, injected into specific muscles in the pivotal clinical trial.

Table 22: XEOMIN 120 Units Initial Dose (Units and % of the Total Dose) by Unilateral Muscle Injected During Double Blind Pivotal Phase 3 Study
 |  | XEOMIN Dose Injected
 | Number of Patients Injected Per Muscle | Median XEOMIN Units | 75th percentile XEOMIN Units
Sternocleidomastoid | 63 | 25 | 35
Splenius capitis/ Semispinalis capitis | 78 | 48 | 63
Trapezius | 55 | 25 | 38
Levator scapulae | 49 | 25 | 25
Scalenus (medius and anterior) | 27 | 20 | 25

Most patients received a total of 2-10 injections into the selected muscles. Patients were assessed by telephone at one week post-injection, during clinic visits at Weeks 4 and 8, and then by telephone assessments or clinic visits every two weeks up to Week 20.

The mean age of the study patients was 53 years, 66% of the patients were women, and 91% were White. At study baseline, 61% of patients had previously received a botulinum toxin as treatment for cervical dystonia. The study was completed by 94% of study patients. Three patients discontinued the study prematurely due to adverse events: two patients in the 240 Unit group experienced musculoskeletal pain and muscle weakness, and one patient in the 120 Unit group experienced nausea and dizziness.

The primary efficacy endpoint was the change in the TWSTRS total score from baseline to Week 4 post-injection, in the intent-to-treat (ITT) population, with missing values replaced by the patient's baseline value. TWSTRS evaluates the severity of dystonia, patient-perceived disability from dystonia, and pain, with a range of possible scores from 0 to 85. The mean change in the total TWSTRS score was significantly greater for both XEOMIN groups than for the placebo group (Table 23).

Table 23: Change in TWSTRS Score at Week 4 in Patients with Cervical Dystonia (Double Blind Pivotal Phase 3 Study)
TWSTRS Assessment | XEOMIN 240 Units (N=78) | XEOMIN 120 Units (N=81) | Placebo (N =74)
Total TWSTRS at baseline | 42.1 | 42.6 | 41.8
Total TWSTRS at Week 4 | 31.2 | 32.7 | 39.5
Mean (SD) Change in TWSTRS score from baseline to Week 4 | -10.9 (11.7) | -9.9 (10.4) | -2.2 (7.3)
Mean difference from placebo (95% CI) | -9.0 (-12.0, -5.9) | -7.5 (-10.4, -4.6)
p-value [p-value(s) are from ANCOVA model.] versus placebo | <0.001 | <0.001
SD = Standard Deviation, CI = Confidence Interval.

The efficacy of XEOMIN was similar in patients who were botulinum toxin naïve and those who had received botulinum toxin prior to this study.

Examination of age and gender subgroups did not identify differences in response to XEOMIN among these subgroups.

14.4 Blepharospasm

Treatment-Naïve Patients

The efficacy and safety of XEOMIN for the treatment of blepharospasm in treatment-naïve patients were evaluated in Study 1 (NCT01896895), a randomized, double-blind, placebo-controlled, multi-center trial in a total of 61 patients. Patients had a clinical diagnosis of blepharospasm, with a baseline Jankovic Rating Scale (JRS) severity subscore ≥2. Patients were defined as treatment-naïve if at least 12 months had passed since their last botulinum toxin treatment for blepharospasm. During the placebo-controlled phase, a fixed total dose of 25 Units XEOMIN (n=22), 50 Units XEOMIN (n=19), or placebo (n=20) was administered intramuscularly at 6 injection sites per eye (Figure 9). Of the 61 patients randomized, 55 patients completed the placebo-controlled phase. Patients only continued to the open-label extension (OLEX) period if they had a confirmed need for a re-injection by week 20 of the placebo-controlled phase. A total of 39 patients entered and completed the OLEX phase.

The primary efficacy variable was the change from baseline in JRS Severity subscore determined at Week 6 after the injection. The 50 Unit treatment group demonstrated statistically significant improvements compared to placebo, with a difference of -1.2 (p=0.0004). The change from baseline in the JRS Severity subscore for the 25 Unit treatment group 6 weeks after the injection was not statistically significant, with a difference of -0.5 (p=0.1452) compared to placebo (see Figure 9).

Figure 9: Frequency Distribution of Changes from Baseline JRS Severity Subscore at Week 6 for Treatment-Naïve Patients

Pre-Treated Patients

The efficacy and safety of XEOMIN for the treatment of blepharospasm patients pre-treated with onabotulinumtoxinA (Botox) were evaluated in Study 2 (NCT00406367), a randomized, double-blind, placebo-controlled, multi-center trial in a total of 109 patients. Patients had a clinical diagnosis of benign essential blepharospasm, with baseline JRS Severity subscore ≥2, and a stable satisfactory therapeutic response to previous administrations of onabotulinumtoxinA (Botox). At least 10 weeks had to have elapsed since the most recent onabotulinumtoxinA administration. Patients with any significant neuromuscular disease that might interfere with the study were excluded from enrollment. Patients were randomized (2:1) to receive a single administration of XEOMIN (n=75) or placebo (n=34). Each patient in the XEOMIN group received a XEOMIN treatment (dose, volume, dilution, and injection sites per muscle) that was similar to the most recent onabotulinumtoxinA injection sessions prior to study entry. The highest dose permitted in this study was 100 Units (50 Units per eye); the mean XEOMIN dose was 33 Units per eye.

In Table 24 the most frequently injected sites, the median dose per injection site, and the median number (and range) of injection sites per eye are presented.

Table 24: Median Dose and Median Number of Injection Sites per Eye (Blepharospasm)
Injection Area | Median Units XEOMIN | Median Number of Injection Sites (Min-Max)
Temporal Area | 13 | 2 (1 – 6)
Eyebrow Area | 5 | 1 (1 – 4)
Upper Lid Area | 10 | 2 (1 – 4)
Lower Lid Area | 8 | 2 (1 – 3)
Orbital Rim | 5 | 1 (1 – 3)

Patients were assessed during clinic visits at Weeks 3 and 6, and then by telephone or at clinic visits every two weeks up to Week 20.

The mean age of the study patients was 62 years, 65% of the patients were women, and 83% were White. The study was completed by 94% of study patients. Approximately one third of patients had other dystonic phenomena; in all but 1% this was limited to facial, cervical, perioral and mandibular muscles. No patients discontinued the study prematurely due to adverse events.

The primary efficacy endpoint was the change in the JRS Severity subscore from baseline to Week 6 post-injection, in the intent-to-treat (ITT) population, with missing values replaced by the patient's most recent value (i.e., last observation carried forward). In the ITT population, the difference between the XEOMIN group and the placebo group in the change of the JRS Severity subscore from baseline to Week 6 was -1.0 (95% CI -1.4; -0.5) points. Comparison of the XEOMIN group to the placebo group was statistically significant at p<0.001.

Figure 10: Frequency Distribution of Changes from Baseline JRS Severity Subscore at Week 6

Examination of age and gender subgroups did not identify substantial differences in response to XEOMIN among these subgroups.

14.5 Upper Facial Lines (Glabellar Lines, Horizontal Forehead Lines, and Lateral Canthal Lines)

Two randomized, double-blind, multi-center, placebo-controlled clinical trials, Trial 1071 (NCT04594213) and Trial 1070 (NCT04622254), were conducted to evaluate XEOMIN for use in the simultaneous intramuscular treatment of upper facial lines (GL, HFL, and LCL). Each trial included an extension period with two additional open-label treatment cycles. In these two trials a total of 730 adult subjects with GL, HFL, and LCL of at least moderate severity at maximum frown as assessed by the investigator and subject were randomized and treated.

In Trial 1071, a total of 362 subjects were randomized and treated. Of the randomized subjects, 179 subjects were treated with XEOMIN in all three treatment areas (receiving 64 U in total: 20 in GL, 20 U in HFL, 24 U in LCL area), 92 subjects were treated with XEOMIN in the GL and HFL areas (receiving 20 U in the GL area and 20 U in HFL area), and 91 subjects were treated with placebo (receiving equal volume of placebo).

In Trial 1070, a total of 368 subjects were randomized and treated. Of the randomized subjects, 184 subjects were treated with XEOMIN in all three treatment area (receiving 64 U in total: 20 in GL, 20 U in HFL, 24 U in LCL area), 90 subjects were treated with XEOMIN in the LCL area (receiving 24 U in LCL area, 12 U per side), and 94 subjects were treated with placebo (receiving equal volume of placebo).

The mean age of the 730 treated and randomized subjects was 46.5 years. The majority of subjects were female (84%) and White (92%). Fifteen percent (15%) of subjects identified as Hispanic or Latino.

For both trials, the severity of upper facial lines (GL, HFL, and LCL) was assessed at maximum contraction using the 5-point photonumerical Merz Aesthetic Scales (MAS; 0=none, 1= mild, 2=moderate, 3=severe, 4=very severe). The MAS assessment was performed independently by both investigators and subjects. The primary timepoint was Day 30 following the first treatment.

For each upper facial area (GL, HFL, or LCL), treatment success was defined as a score of 0 (none) or 1 (mild) and at least two-grade improvement from baseline to Day 30 as rated on the corresponding scale for GL, HFL, and LCL at maximum contraction as assessed by both the investigator and the subject. The percentage of subjects with treatment success in each treatment area is presented in Table 25.

Table 25. Treatment Success at Day 30 in Adults with Upper Facial Lines (GL/HFL/LCL) in Trial 1071 and Trial 1070
 | Trial 1071 |  |  | Trial 1070
 | XEOMIN (20 Units GL/ 20 Units HFL/ 24 Units LCL) | XEOMIN (20 Units GL/ 20 Units HFL) | Placebo | XEOMIN (20 Units GL/ 20 Units HFL/ 24 Units LCL) | XEOMIN (24 Units LCL) N=90 | Placebo
 | N=179 |  | N=91 |  |  | N=94
 |  | N=92 |  | N=184
GL | 53% | 53% | 0% | 49% | - | 0%
HFL | 67% | 62% | 0% | 58% | - | 0%
LCL | 53% | - | 0% | 33% | 24% | 0%

Glabellar Lines

Two identically designed randomized, double-blind, multi-center, placebo controlled clinical trials (Studies GL-1 and GL-2) were conducted to evaluate XEOMIN for use in the temporary improvement of moderate to severe glabellar lines. The trials enrolled 547 healthy adult patients with glabellar lines of at least moderate severity at maximum frown. Three hundred sixty six (366) subjects were treated with 20 Units of XEOMIN and 181 subjects received placebo. Subjects were excluded if they had marked ptosis, deep dermal scarring, or an inability to lessen glabellar lines, even by physically spreading them apart. The mean age of trial subjects was 46 years. The majority of subjects were female (86% and 93% in Studies GL-1 and GL-2, respectively), and predominantly White (89% and 65% respectively). The trial subjects received either 20 Units of XEOMIN or an equal amount of placebo. The total dose was delivered in 5 equally divided intramuscular injections of 4 Units each to specific sites (see Figure 7). Subjects were followed up for 120 days.

Investigators and subjects assessed efficacy at maximum frown on Day 30 of treatment using a 4-point scale (0=none, 1=mild, 2=moderate, 3=severe). Composite treatment success was defined as a 2-grade improvement on this scale compared to baseline for both the investigator's and subject's assessments on Day 30. The percentage of subjects with treatment success was greater on the XEOMIN arm than the placebo arm at Day 30 in both trials (see Table 26).

Table 26: Treatment Success at Day 30 (at Least 2 Grades Improvement from Baseline at Maximum Frown) in Adults with GL in Studies GL-1 and GL-2
 | GL-1 |  | GL-2
 | XEOMIN (N=184) | Placebo (N=92) | XEOMIN (N=182) | Placebo (N=89)
Composite Treatment Success [Success on both the Investigator and Subject Assessments] | 111 (60%) | 0 (0%) | 87 (48%) | 0 (0%)
Investigator Assessment | 141 (77%) | 0 (0%) | 129 (71%) | 0 (0%)
Subject Assessment | 120 (65%) | 0 (0%) | 101 (55%) | 1 (1%)

16 HOW SUPPLIED/STORAGE AND HANDLING

How Supplied

XEOMIN for injection is a sterile white to off-white lyophilized powder supplied in Type 1 borosilicate glass single-dose vials with tamper-proof aluminum seals and bromobutyl rubber closures that are not made with natural rubber latex in the following pack sizes:

Upper Limb Spasticity and Cervical Dystonia

Package | XEOMIN 50 Units | XEOMIN 100 Units | XEOMIN 200 Units
Carton with one single-dose vial | NDC 0259-1605-01 | NDC 0259-1610-01 | NDC 0259-1620-01

Chronic Sialorrhea and Blepharospasm

Package | XEOMIN 50 Units | XEOMIN 100 Units
Carton with one single-dose vial | NDC 0259-1605-01 | NDC 0259-1610-01

Upper Facial Lines (Glabellar Lines, Horizontal Forehead Lines, and Lateral Canthal Lines)

Package | XEOMIN 50 Units | XEOMIN 100 Units
Carton with one single-dose vial | NDC 46783-161-01 | NDC 46783-160-01

Storage and Handling

Store unopened vials of XEOMIN at or below 25°C (77°F). Refrigeration of unopened vials is not required. Do not use after the expiration date on the vial. Reconstituted XEOMIN may be stored in a refrigerator at 2°C to 8°C (36°F to 46°F) for up to 24 hours until time of use [see Dosage and Administration (2.7)].

17 PATIENT COUNSELING INFORMATION

Advise the patient to read the FDA-approved patient labeling (Medication Guide).

Swallowing, Speaking, or Breathing Difficulties or Other Unusual Symptoms

Advise patients to inform their healthcare provider if they develop any unusual symptoms, including difficulty with swallowing, speaking, or breathing, or if any existing symptom worsens [see Boxed Warning and Warnings and Precautions (5.1, 5.4)]. Inform patients of the risk of aspiration.

Ability to Operate Machinery or Vehicles

Counsel patients that if loss of strength, muscle weakness, blurred vision, or drooping eyelids occur, they should avoid driving a car or engaging in other potentially hazardous activities.

Corneal Exposure, Corneal Ulceration, and Ectropion in Patients Treated for Blepharospasm

Inform patients that injections of XEOMIN may cause reduced blinking or effectiveness of blinking, and that they should seek immediate medical attention if eye pain or irritation occurs following treatment [see Warnings and Precautions (5.5)].

Manufactured by:
Merz Pharmaceuticals GmbH
Eckenheimer Landstrasse 100
Frankfurt Germany
U.S. License Number 1830

Distributed by:
Merz Pharmaceuticals, LLC
6601 Six Forks Road, Suite 430
Raleigh, NC 27615

and

Merz North America, Inc.
4133 Courtney Street, Suite 10
Franksville, WI 53126

©2024 Merz Pharmaceuticals, LLC
XEOMIN® is a registered trademark of Merz Pharma GmbH & Co KGaA.
All trademarks are the property of their respective owners.
Patent www.merztherapeutics.com/us/patents/

IN00180-02

MEDICATION GUIDE
XEOMIN® (Zeo-min)
(incobotulinumtoxinA)
for injection, for intramuscular or intraglandular use

What is the most important information I should know about XEOMIN?

XEOMIN may cause serious side effects that can be life-threatening. Call your doctor or get medical help right away if you have any of these problems after treatment with XEOMIN:

- Problems with swallowing, speaking, or breathing. These problems can happen hours to weeks after an injection of XEOMIN if the muscles that you use to breathe and swallow become weak after the injection. Death can happen as a complication if you have severe problems with swallowing or breathing after treatment with XEOMIN.
  - People with certain breathing problems may need to use muscles in their neck to help them breathe. These people may be at greater risk for serious breathing problems with XEOMIN.
  - Swallowing problems may last for several months. People who cannot swallow well may need a feeding tube to receive food and water. If swallowing problems are severe, food or liquids may go into your lungs. People who already have swallowing or breathing problems before receiving XEOMIN have the highest risk of getting these problems.
- Spread of toxin effects. In some cases, the effect of botulinum toxin may affect areas of the body away from the injection site and cause symptoms of a serious condition called botulism. The symptoms of botulism include:

- loss of strength and muscle weakness all over the body
- double vision
- blurred vision and drooping eyelids
- hoarseness or change or loss of voice

- trouble saying words clearly
- loss of bladder control
- trouble breathing
- trouble swallowing

These symptoms can happen hours to weeks after you receive an injection of XEOMIN

These problems could make it unsafe for you to drive a car or do other dangerous activities. See "What should I avoid while receiving XEOMIN?"

What is XEOMIN?

XEOMIN is a prescription medicine:

- that is injected into glands that make saliva and is used to treat long-lasting (chronic) drooling (sialorrhea) in adults and in children 2 to 17 years of age.
- that is injected into muscles and used to:
- treat increased muscle stiffness in the arm because of upper limb spasticity in adults.
- treat increased muscle stiffness in the arm in children 2 to 17 years of age with upper limb spasticity, excluding spasticity caused by cerebral palsy.
- treat the abnormal head position and neck pain with cervical dystonia (CD) in adults.
- treat abnormal spasm of the eyelids (blepharospasm) in adults.
- improve the appearance of upper facial lines (glabellar lines, horizontal forehead lines, and lateral canthal lines) (treated simultaneously or individually) for a short period of time (temporary) in adults.

It is not known if XEOMIN is safe and effective in children younger than:

- 2 years of age for the treatment of chronic sialorrhea
- 2 years of age for the treatment of upper limb spasticity
- 18 years of age for the treatment of upper facial lines (glabellar lines, horizontal forehead lines, and lateral canthal lines), cervical dystonia, or blepharospasm

Do not take XEOMIN if you:

- are allergic to XEOMIN or any of the ingredients in XEOMIN. See the end of this Medication Guide for a list of ingredients in XEOMIN.
- had an allergic reaction to any other botulinum toxin products
- have a skin infection at the planned injection site.

Before receiving XEOMIN, tell your doctor about all of your medical conditions, including if you:

- have a disease that affects your muscles and nerves (such as amyotrophic lateral sclerosis [ALS or Lou Gehrig's disease], myasthenia gravis or Lambert-Eaton syndrome). See "What is the most important information I should know about XEOMIN?"
- have had any side effects from any other botulinum toxin in the past.
- have a breathing problem, such as asthma or emphysema.
- have a history of swallowing problems or inhaling food or fluid into your lungs (aspiration).
- have drooping eyelids.
- have had eye surgery.
- have had surgery on your face.
- are pregnant or plan to become pregnant. It is not known if XEOMIN can harm your unborn baby.
- are breastfeeding or plan to breastfeed. It is not known if XEOMIN passes into your breast milk.

Tell your doctor about all the medicines you take, including prescription and over-the-counter medicines, vitamins and herbal supplements. Talk to your doctor before you take any new medicines after you receive XEOMIN.

Using XEOMIN with certain other medicines may cause serious side effects. Do not start any new medicines until you have told your doctor that you have received XEOMIN in the past. Especially tell your doctor if you:

- have received any other botulinum toxin product in the last four months.
- have received injections of botulinum toxin in the past. Be sure your doctor knows exactly which product you received. The dose of XEOMIN may be different from other botulinum toxin products that you have received.
- have recently received an antibiotic by injection or inhalation.
- take muscle relaxants.
- take an allergy or cold medicine.
- take a sleep medicine.

Ask your doctor if you are not sure if you take any of the medicines listed above.

Know the medicines you take. Keep a list of your medicines with you to show your doctor and pharmacist each time you get a new medicine.

How will I receive XEOMIN?

- XEOMIN is a shot (injection) that your doctor will give you.
- XEOMIN is injected into your affected muscles or glands.
- Your doctor may change your dose of XEOMIN during treatment.

What should I avoid while taking XEOMIN?

XEOMIN may cause loss of strength or general muscle weakness, blurred vision, or drooping eyelids within hours to weeks of taking XEOMIN. If this happens, do not drive a car, operate machinery, or do other dangerous activities. See "What is the most important information I should know about XEOMIN? "

What are the possible side effects of XEOMIN?

XEOMIN may cause serious side effects, including:

See "What is the most important information I should know about XEOMIN?"

- Injury to the cornea (the clear front surface of the eye) in people treated for blepharospasm. People who receive XEOMIN to treat spasm of the eyelid may have reduced blinking that can cause a sore on their cornea or other problems of the cornea. Call your healthcare provider or get medical care right away if you have eye pain or irritation after treatment with XEOMIN.
- XEOMIN may cause other serious side effects including allergic reactions. Symptoms of an allergic reaction to XEOMIN may include: itching, rash, redness, swelling, wheezing, trouble breathing, or dizziness or feeling faint. Tell your doctor or get medical help right away if you get wheezing or trouble breathing, or if you get dizzy or faint.

The most common side effects of XEOMIN in adults with chronic sialorrhea include:

- needing to have a tooth pulled (extracted)
- dry mouth

- diarrhea
- high blood pressure

The most common side effects of XEOMIN in children 2 to 17 years of age with chronic sialorrhea include:

- bronchitis
- nausea

- headache
- vomiting

The most common side effects of XEOMIN in adults with upper limb spasticity include:

- seizure
- nasal congestion, sore throat and runny nose

- dry mouth
- upper respiratory infection

The most common side effects of XEOMIN in children 2 to 17 years of age with upper limb spasticity include:

- nasal congestion, sore throat, and runny nose
- bronchitis

The most common side effects of XEOMIN in adults with cervical dystonia include:

- difficulty swallowing
- neck pain
- muscle weakness

- pain at the injection site
- muscle and bone pain

The most common side effects of XEOMIN in adults with blepharospasm include:

- drooping of the eyelid
- dry eye

- vision problems
- dry mouth

The most common side effect of Xeomin in adults with upper facial lines (glabellar lines, horizontal forehead lines, and lateral canthal lines) include:

- injection site bruising

These are not all the possible side effects of XEOMIN.

Call your doctor for medical advice about side effects. You may report side effects to FDA at 1-800-FDA-1088.

General information about the safe and effective use of XEOMIN.

Medicines are sometimes prescribed for purposes other than those listed in a Medication Guide. You can ask your pharmacist or doctor for information about XEOMIN that is written for health professionals.

What are the ingredients in XEOMIN?

Active ingredient: botulinum toxin type A

Inactive ingredients: human albumin and sucrose

Manufactured by: Merz Pharmaceuticals GmbH, Eckenheimer Landstrasse 100, Frankfurt Germany U.S. License Number 1830
Distributed by: Merz Pharmaceuticals, LLC, 6601 Six Forks Road, Suite 430, Raleigh, NC 27615 and Merz North America, Inc. 4133 Courtney Street, Suite 10, Franksville, WI 53126
©2024 Merz Pharmaceuticals, LLC, XEOMIN® is a registered trademark of Merz Pharma GmbH & Co KGaA.
Patent www.merztherapeutics.com/us/patents/

IN00180-02

This Medication Guide has been approved by the U. S. Food and Drug Administration.

Revised: 7/2024

PRINCIPAL DISPLAY PANEL - 50 Unit Vial Carton

Rx Only
1 vial
NDC 46783-161-01

incobotulinumtoxinA
XEOMIN®

FOR INJECTION
50 units/vial

For Intramuscular Use

Dispense the enclosed Medication Guide to
each patient. One single-dose vial per carton.
Discard unused portion.

50
units/vial

WARNING: Dosing units of botulinum toxins are not
interchangeable between commercial products.

MERZ AESTHETICS®

PRINCIPAL DISPLAY PANEL - 100 Unit Vial Carton

Rx Only
1 vial
NDC 46783-160-01

incobotulinumtoxinA
XEOMIN®

FOR INJECTION
100 units/vial

For Intramuscular Use

Dispense the enclosed Medication Guide to
each patient. One single-dose vial per carton.
Discard unused portion.

100
units/vial

WARNING: Dosing units of botulinum toxins are not
interchangeable between commercial products.

MERZ AESTHETICS®

PRINCIPAL DISPLAY PANEL - 50 Unit Vial Carton - NDC 46783-165-01

Rx Only
1 vial
NDC 46783-165-01

incobotulinumtoxinA
XEOMIN®

FOR INJECTION
50 units/vial

Physician Sample - Not for Resale

For Intramuscular Use

Dispense the enclosed Medication Guide to
each patient. One single-dose vial per carton.
Discard unused portion.

50
units/vial

WARNING: Dosing units of botulinum toxins are not
interchangeable between commercial products.

MERZ AESTHETICS®